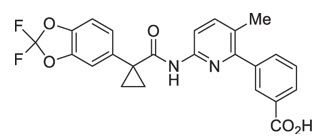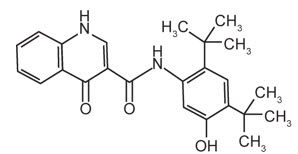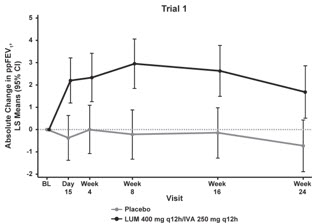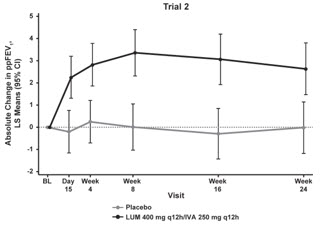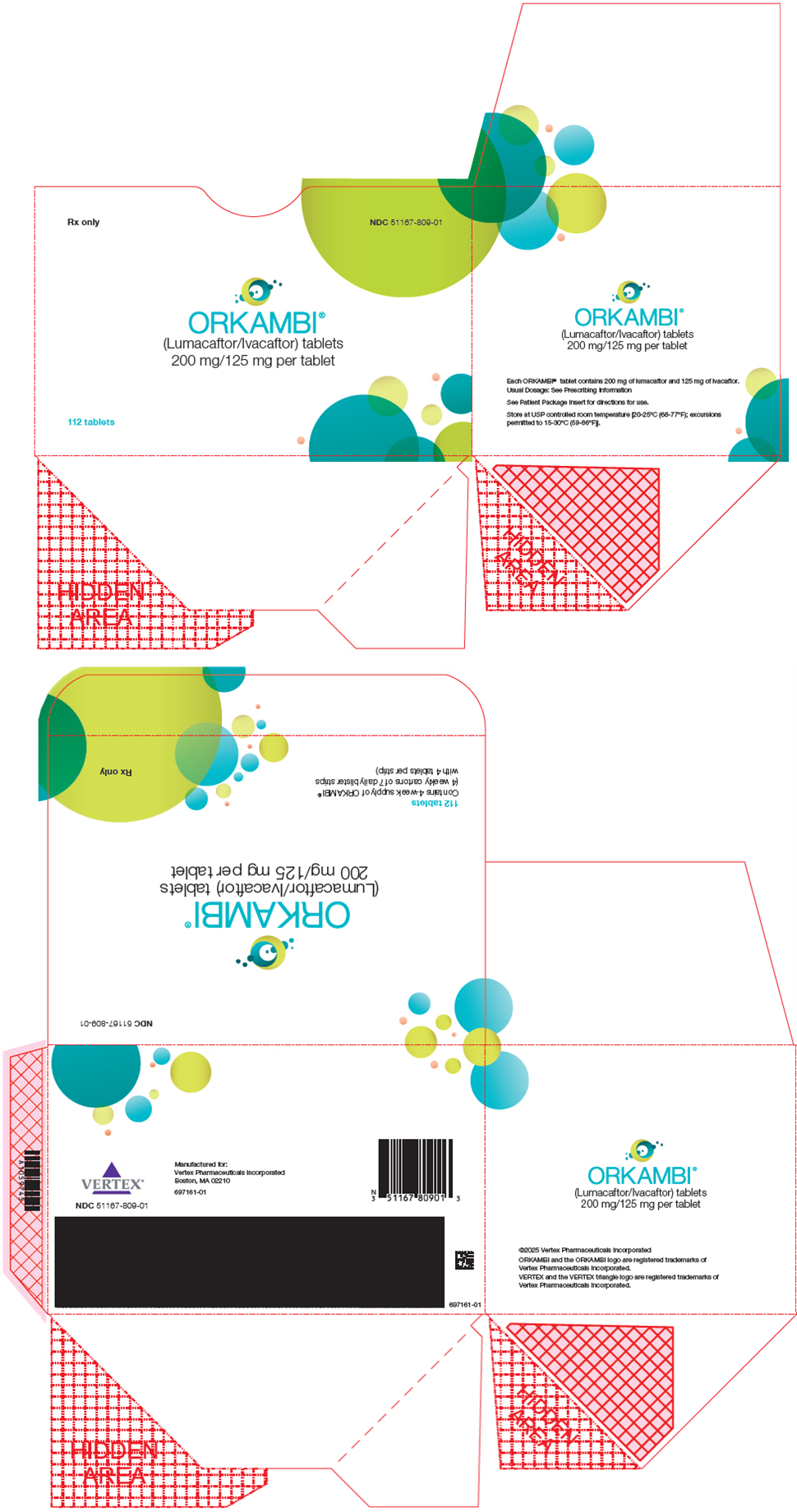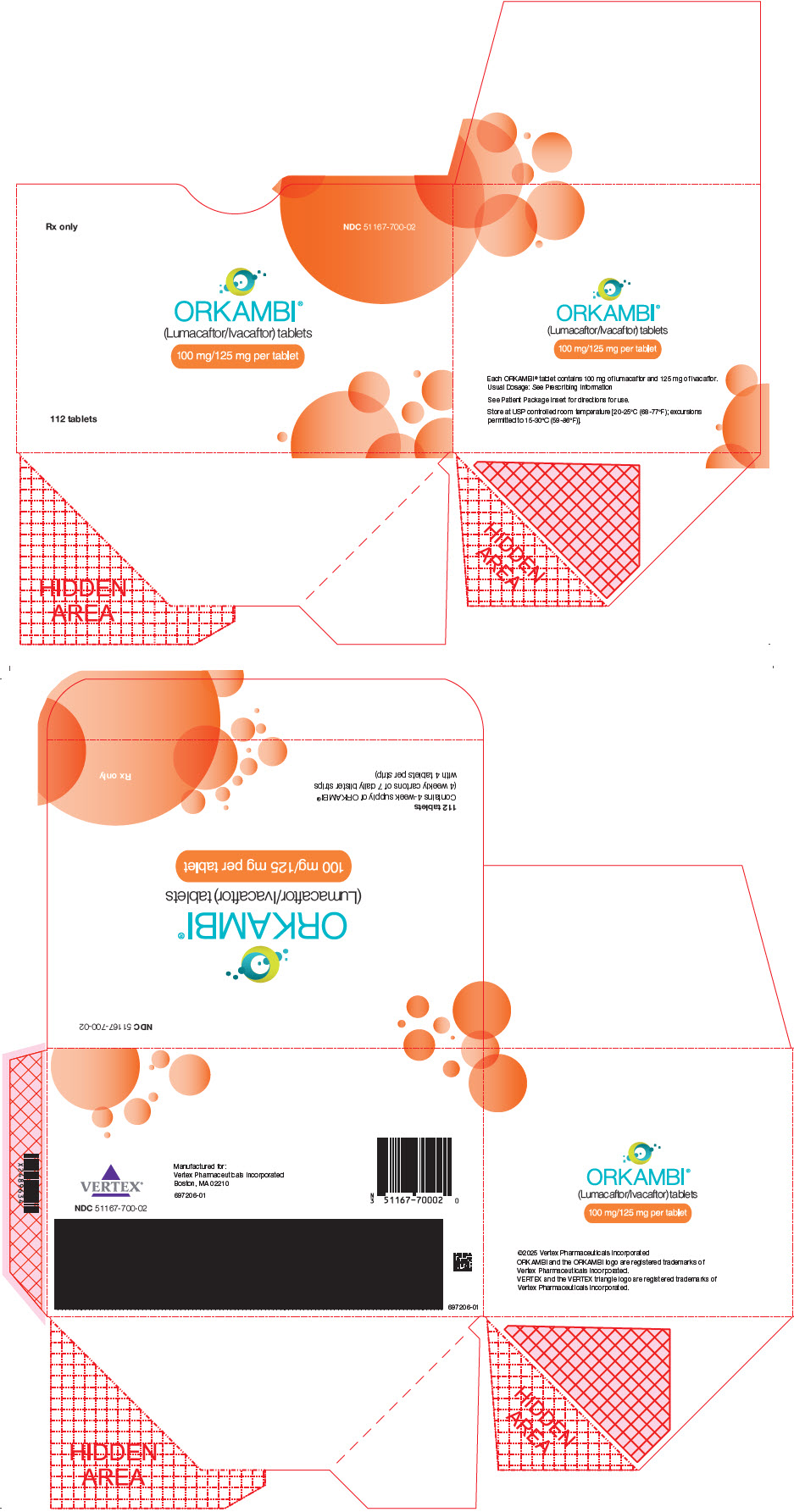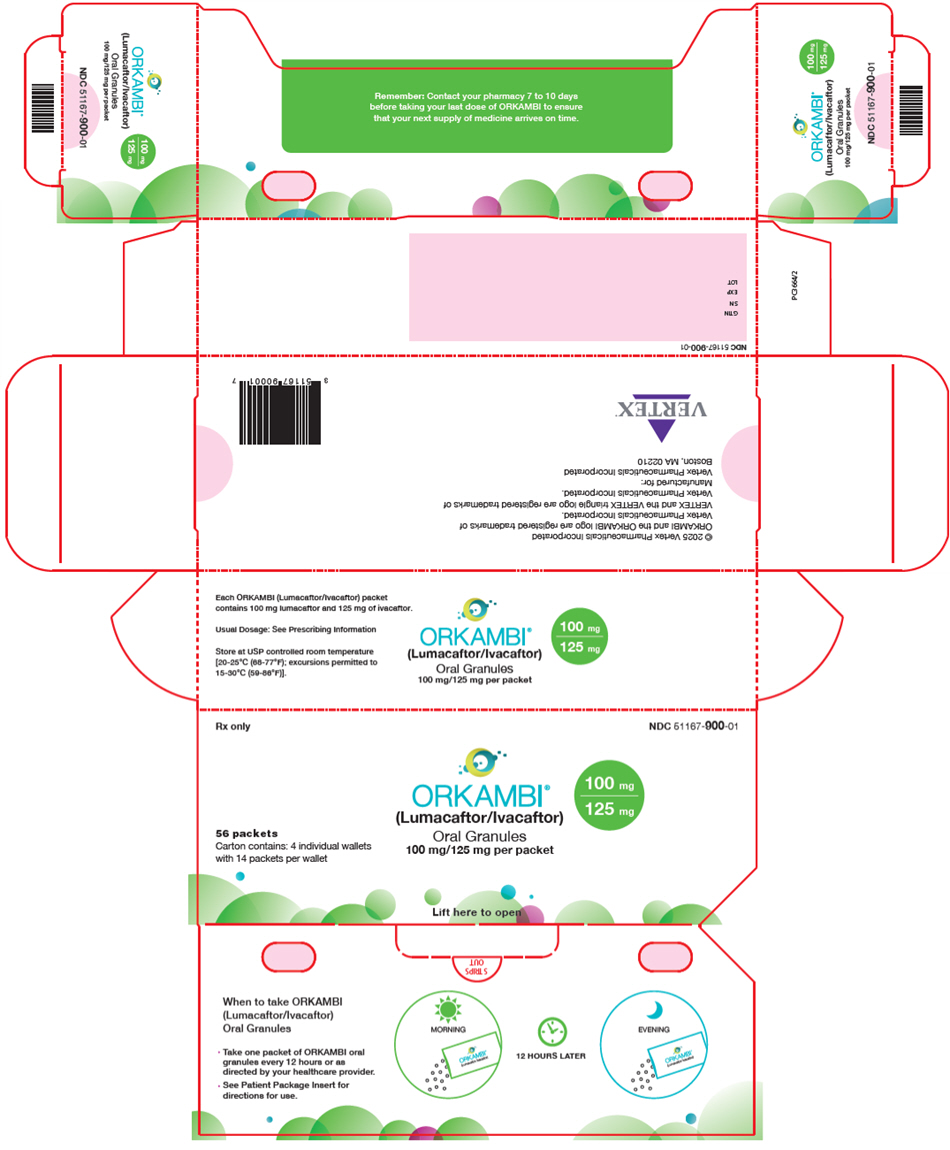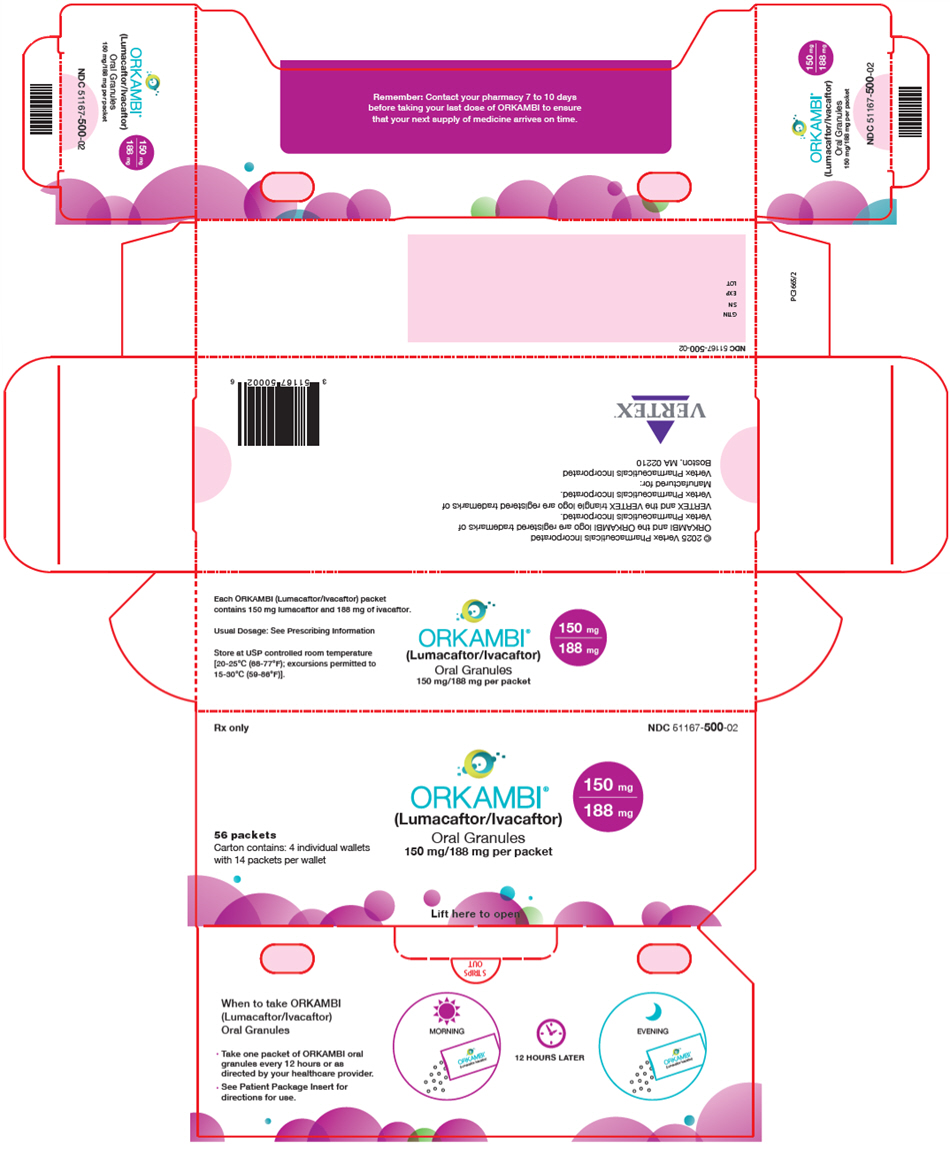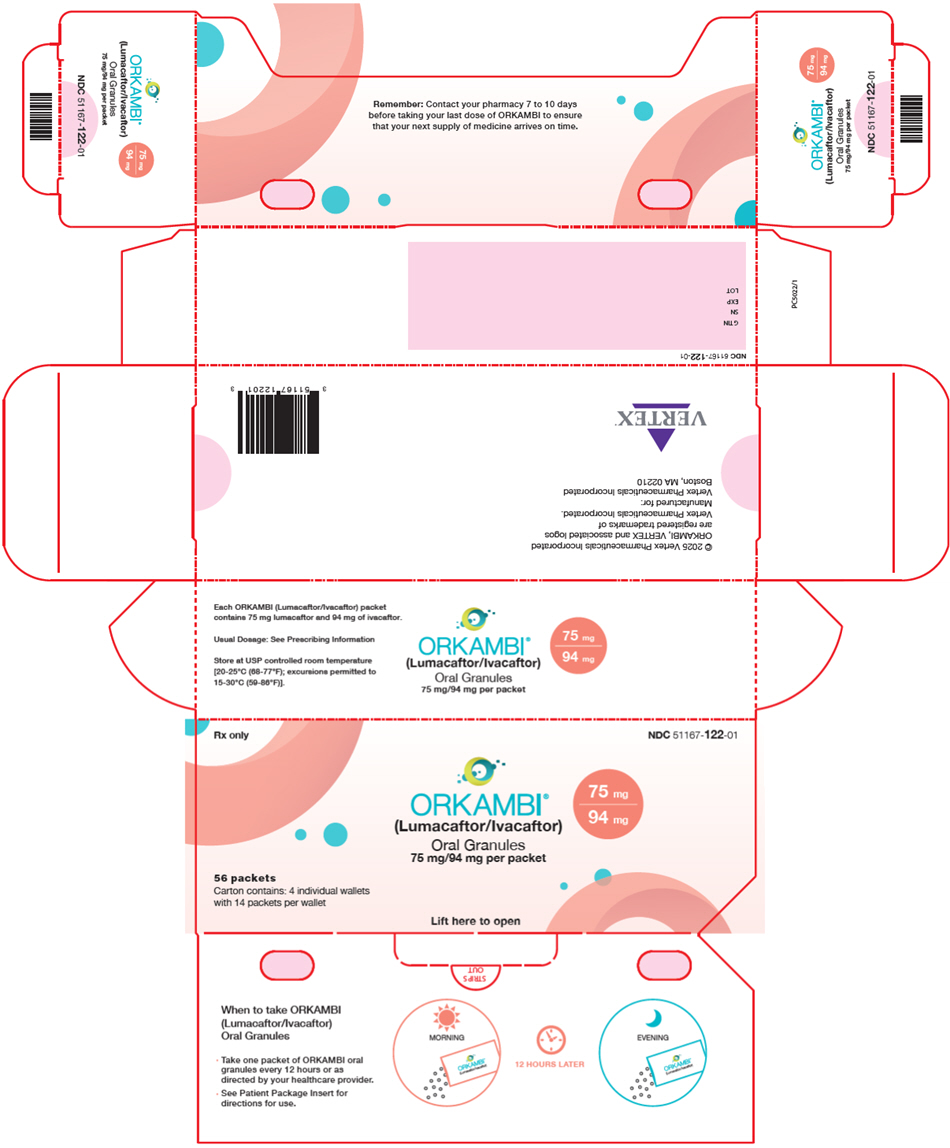 DRUG LABEL: ORKAMBI
NDC: 51167-809 | Form: TABLET, FILM COATED
Manufacturer: Vertex Pharmaceuticals Incorporated
Category: prescription | Type: HUMAN PRESCRIPTION DRUG LABEL
Date: 20251001

ACTIVE INGREDIENTS: lumacaftor 200 mg/1 1; ivacaftor 125 mg/1 1
INACTIVE INGREDIENTS: MICROCRYSTALLINE CELLULOSE; CROSCARMELLOSE SODIUM; HYPROMELLOSE ACETATE SUCCINATE 06081224 (3 MPA.S); MAGNESIUM STEARATE; POVIDONE, UNSPECIFIED; SODIUM LAURYL SULFATE; CARMINIC ACID; FD&C Blue No. 1; FD&C Blue No. 2; POLYETHYLENE GLYCOL 3350; POLYVINYL ALCOHOL, UNSPECIFIED; TALC; TITANIUM DIOXIDE; AMMONIA; FERROSOFERRIC OXIDE; PROPYLENE GLYCOL; SHELLAC

HIGHLIGHTS OF PRESCRIBING INFORMATION

These highlights do not include all the information needed to use ORKAMBI safely and effectively. See full prescribing information for ORKAMBI.
ORKAMBI® (lumacaftor and ivacaftor) tablets, for oral use
ORKAMBI® (lumacaftor and ivacaftor) oral granules
Initial U.S. Approval: 2015

RECENT MAJOR CHANGES

Warnings and Precautions, Intracranial Hypertension (5.4) | 09/2025

1 INDICATIONS AND USAGE

ORKAMBI is a combination of ivacaftor, a cystic fibrosis transmembrane conductance regulator (CFTR) potentiator, and lumacaftor, indicated for the treatment of cystic fibrosis (CF) in patients aged 1 year and older who are homozygous for the F508del mutation in the CFTR gene. If the patient's genotype is unknown, an FDA-cleared CF mutation test should be used to detect the presence of the F508del mutation on both alleles of the CFTR gene. (1)

Limitations of Use:

The efficacy and safety of ORKAMBI have not been established in patients with CF other than those homozygous for the F508del mutation. (1)

2 DOSAGE AND ADMINISTRATION

Age Group | Weight | Dose | Administration
1 through 2 years | 7 kg to < 9 kg | 1 packet of lumacaftor 75 mg/ivacaftor 94 mg granules | Mixed with one teaspoon (5 mL) of soft food or liquid and administered orally every 12 hours with fat-containing food
1 through 2 years | 9 kg to < 14 kg | 1 packet of lumacaftor 100 mg/ivacaftor 125 mg granules | Mixed with one teaspoon (5 mL) of soft food or liquid and administered orally every 12 hours with fat-containing food
1 through 2 years | ≥14 kg | 1 packet of lumacaftor 150 mg/ivacaftor 188 mg granules | Mixed with one teaspoon (5 mL) of soft food or liquid and administered orally every 12 hours with fat-containing food
2 through 5 years | <14 kg | 1 packet of lumacaftor 100 mg/ivacaftor 125 mg granules | Mixed with one teaspoon (5 mL) of soft food or liquid and administered orally every 12 hours with fat-containing food
2 through 5 years | ≥14 kg | 1 packet of lumacaftor 150 mg/ivacaftor 188 mg granules | Mixed with one teaspoon (5 mL) of soft food or liquid and administered orally every 12 hours with fat-containing food
6 through 11 years | - | 2 tablets of lumacaftor 100 mg/ivacaftor 125 mg (lumacaftor 200 mg/ivacaftor 250 mg per dose) | Taken orally every 12 hours with fat-containing food
12 years and older | - | 2 tablets of lumacaftor 200 mg/ivacaftor 125 mg (lumacaftor 400 mg/ivacaftor 250 mg per dose) | Taken orally every 12 hours with fat-containing food

- Reduce dosage in patients with moderate or severe hepatic impairment. (2.2, 8.6, 12.3)
- When initiating ORKAMBI in patients taking strong CYP3A inhibitors, reduce ORKAMBI dosage for the first week of treatment. (2.3, 7.1, 12.3)

3 DOSAGE FORMS AND STRENGTHS

- Tablets: lumacaftor 100 mg and ivacaftor 125 mg; lumacaftor 200 mg and ivacaftor 125 mg. (3)
- Oral granules: Unit-dose packets of lumacaftor 75 mg and ivacaftor 94 mg; lumacaftor 100 mg and ivacaftor 125 mg; lumacaftor 150 mg and ivacaftor 188 mg. (3)

4 CONTRAINDICATIONS

- None. (4)

5 WARNINGS AND PRECAUTIONS

- Use in patients with advanced liver disease: ORKAMBI should be used with caution in these patients and only if the benefits are expected to outweigh the risks. If ORKAMBI is used in these patients, they should be closely monitored after the initiation of treatment and the dosage should be reduced. Liver function decompensation, including liver failure leading to death, has been reported in CF patients with pre-existing cirrhosis with portal hypertension. (2.2, 5.1, 6.1)
- Liver-related events: Elevated transaminases (ALT/AST) have been observed in some cases associated with elevated bilirubin. Measure serum transaminases and bilirubin before initiating ORKAMBI, every 3 months during the first year of treatment, and annually thereafter. For patients with a history of ALT, AST, or bilirubin elevations, more frequent monitoring should be considered. Interrupt dosing in patients with ALT or AST >5 × upper limit of normal (ULN), or ALT or AST >3 × ULN with bilirubin >2 × ULN. Following resolution, consider the benefits and risks of resuming dosing. (5.2, 6.1)
- Hypersensitivity reactions: Angioedema and anaphylaxis have been reported with ORKAMBI in the postmarketing setting. Initiate appropriate therapy in the event of a hypersensitivity reaction. (5.3)
- Intracranial hypertension: Intracranial hypertension (IH) has been reported in the postmarketing setting with the use of ORKAMBI. If an unusual headache or visual disturbances occur during treatment, and IH is suspected, interrupt ORKAMBI and refer for prompt medical evaluation. (5.4)
- Respiratory events: Chest discomfort, dyspnea, and respiration abnormal were observed more commonly during initiation of ORKAMBI. Clinical experience in patients with percent predicted FEV1 (ppFEV1) <40 is limited, and additional monitoring of these patients is recommended during initiation of therapy. (5.5, 6.1)
- Blood pressure: Increased blood pressure has been observed in some patients. Periodically monitor blood pressure in all patients. (5.6, 6.1)
- Drug interactions: Use with sensitive CYP3A substrates or CYP3A substrates with a narrow therapeutic index may decrease systemic exposure of the medicinal products and co-administration is not recommended. Hormonal contraceptives should not be relied upon as an effective method of contraception and their use is associated with increased menstruation-related adverse reactions. Use with strong CYP3A inducers may diminish exposure of ivacaftor, which may diminish its effectiveness; therefore, co-administration is not recommended. (5.7, 6.1, 7, 12.3)
- Cataracts: Non-congenital lens opacities/cataracts have been reported in pediatric patients treated with ORKAMBI and ivacaftor, a component of ORKAMBI. Baseline and follow-up examinations are recommended in pediatric patients initiating ORKAMBI. (5.8)

6 ADVERSE REACTIONS

The most common adverse reactions to ORKAMBI (occurring in ≥5% of patients with CF homozygous for the F508del mutation in the CFTR gene) were dyspnea, nasopharyngitis, nausea, diarrhea, upper respiratory tract infection, fatigue, respiration abnormal, blood creatine phosphokinase increased, rash, flatulence, rhinorrhea, influenza. (6.1)

To report SUSPECTED ADVERSE REACTIONS, contact Vertex Pharmaceuticals Incorporated at 1-877-634-8789 or FDA at 1-800-FDA-1088 or www.fda.gov/medwatch.

7 DRUG INTERACTIONS

See Full Prescribing Information for a complete list. (2.3, 7, 12.3)

FULL PRESCRIBING INFORMATION

1 INDICATIONS AND USAGE

ORKAMBI is indicated for the treatment of cystic fibrosis (CF) in patients aged 1 year and older who are homozygous for the F508del mutation in the CFTR gene. If the patient's genotype is unknown, an FDA-cleared CF mutation test should be used to detect the presence of the F508del mutation on both alleles of the CFTR gene.

Limitations of Use

The efficacy and safety of ORKAMBI have not been established in patients with CF other than those homozygous for the F508del mutation.

2 DOSAGE AND ADMINISTRATION

2.1 Recommended Dosage in Adults and Pediatric Patients Aged 1 Year and Older

The recommended dosage of ORKAMBI in adults and pediatric patients aged one year and older is based on patient's age and weight as described in Table 1.

Table 1: Recommended Oral Dosage of ORKAMBI in Patients Aged 1 Year and Older
Age Group | Weight | ORKAMBI Daily Dose (every 12 hours)
Age Group | Weight | Morning Dose | Evening Dose
1 through 2 years | 7 kg to <9 kg | 1 packet of lumacaftor 75 mg/ivacaftor 94 mg oral granules | 1 packet of lumacaftor 75 mg/ivacaftor 94 mg oral granules
1 through 2 years | 9 kg to <14 kg | 1 packet of lumacaftor 100 mg/ivacaftor 125 mg oral granules | 1 packet of lumacaftor 100 mg/ivacaftor 125 mg oral granules
1 through 2 years | ≥14 kg | 1 packet of lumacaftor 150 mg/ivacaftor 188 mg oral granules | 1 packet of lumacaftor 150 mg/ivacaftor 188 mg oral granules
2 through 5 years | <14 kg | 1 packet of lumacaftor 100 mg/ivacaftor 125 mg oral granules | 1 packet of lumacaftor 100 mg/ivacaftor 125 mg oral granules
2 through 5 years | ≥14 kg | 1 packet of lumacaftor 150 mg/ivacaftor 188 mg oral granules | 1 packet of lumacaftor 150 mg/ivacaftor 188 mg oral granules
6 through 11 years | - | 2 tablets of lumacaftor 100 mg/ivacaftor 125 mg (lumacaftor 200 mg/ivacaftor 250 mg per dose) | 2 tablets of lumacaftor 100 mg/ivacaftor 125 mg (lumacaftor 200 mg/ivacaftor 250 mg per dose)
12 years and older | - | 2 tablets of lumacaftor 200 mg/ivacaftor 125 mg (lumacaftor 400 mg/ivacaftor 250 mg per dose) | 2 tablets of lumacaftor 200 mg/ivacaftor 125 mg (lumacaftor 400 mg/ivacaftor 250 mg per dose)

Administration Instructions for ORKAMBI Oral Granules

The entire content of each packet of oral granules should be mixed with one teaspoon (5 mL) of age-appropriate soft food or liquid and the mixture completely consumed. Some examples of soft foods or liquids include puréed fruits or vegetables, flavored yogurt or pudding, applesauce, water, milk, breast milk, infant formula or juice. Food should be at room temperature or below. Each packet is for single use only. Once mixed, the product has been shown to be stable for one hour, and therefore should be ingested during this period.

Administration with Fat-Containing Food for ORKAMBI Tablets and Oral Granules

A fat-containing meal or snack should be consumed just before or just after dosing for all formulations. Examples of appropriate fat-containing foods include eggs, avocados, nuts, butter, peanut butter, cheese pizza, breast milk, infant formula, whole-milk dairy products (such as whole milk, cheese, and yogurt), etc.

Missed Dose

If a patient misses a dose and remembers the missed dose within 6 hours, the patient should take the dose with fat-containing food. If more than 6 hours elapsed after the recommended dosing time, the patient should skip that dose and resume the normal schedule for the following dose. A double dose should not be taken to make up for the forgotten dose [see Clinical Pharmacology (12.3) and Patient Counseling Information (17)].

2.2 Dosage Adjustment for Patients with Hepatic Impairment

For dosage adjustment for patients with hepatic impairment, refer to Table 2.

Studies have not been conducted in patients with severe hepatic impairment (Child-Pugh Class C), but exposure is expected to be higher than in patients with moderate hepatic impairment. Therefore, use with caution at a maximum dose of 1 tablet in the morning and 1 tablet in the evening or less frequently, or 1 packet of oral granules once daily or less frequently in patients with severe hepatic impairment after weighing the risks and benefits of treatment [see Dosage and Administration (2.1), Use in Specific Populations (8.6), Clinical Pharmacology (12.3), and Patient Counseling Information (17)].

Table 2: Recommended Dosage for Patients with Hepatic Impairment
 | Age Group | Weight | Morning Dose | Evening Dose
Mild (Child-Pugh Class A) | 1 through 2 years | 7 kg to <9 kg | 1 packet of lumacaftor 75 mg/ivacaftor 94 mg oral granules | 1 packet of lumacaftor 75 mg/ivacaftor 94 mg oral granules
Mild (Child-Pugh Class A) | 1 through 2 years | 9 kg to <14 kg | 1 packet of lumacaftor 100 mg/ivacaftor 125 mg oral granules | 1 packet of lumacaftor 100 mg/ivacaftor 125 mg oral granules
Mild (Child-Pugh Class A) | 1 through 2 years | ≥14 kg | 1 packet of lumacaftor 150 mg/ivacaftor 188 mg oral granules | 1 packet of lumacaftor 150 mg/ivacaftor 188 mg oral granules
Mild (Child-Pugh Class A) | 2 through 5 years | <14 kg | 1 packet of lumacaftor 100 mg/ivacaftor 125 mg oral granules | 1 packet of lumacaftor 100 mg/ivacaftor 125 mg oral granules
Mild (Child-Pugh Class A) | 2 through 5 years | ≥14 kg | 1 packet of lumacaftor 150 mg/ivacaftor 188 mg oral granules | 1 packet of lumacaftor 150 mg/ivacaftor 188 mg oral granules
Mild (Child-Pugh Class A) | 6 through 11 years | - | 2 tablets of lumacaftor 100 mg/ivacaftor 125 mg (lumacaftor 200 mg/ivacaftor 250 mg per dose) | 2 tablets of lumacaftor 100 mg/ivacaftor 125 mg (lumacaftor 200 mg/ivacaftor 250 mg per dose)
Mild (Child-Pugh Class A) | 12 years and older | - | 2 tablets of lumacaftor 200 mg/ivacaftor 125 mg (lumacaftor 400 mg/ivacaftor 250 mg per dose) | 2 tablets of lumacaftor 200 mg/ivacaftor 125 mg (lumacaftor 400 mg/ivacaftor 250 mg per dose)
Moderate (Child-Pugh Class B) | 1 through 2 years | 7 kg to <9 kg | 1 packet of lumacaftor 75 mg/ivacaftor 94 mg oral granules | 1 packet of lumacaftor 75 mg/ivacaftor 94 mg oral granules every other day
Moderate (Child-Pugh Class B) | 1 through 2 years | 9 kg to <14 kg | 1 packet of lumacaftor 100 mg/ivacaftor 125 mg oral granules | 1 packet of lumacaftor 100 mg/ivacaftor 125 mg oral granules every other day
Moderate (Child-Pugh Class B) | 1 through 2 years | ≥14 kg | 1 packet of lumacaftor 150 mg/ivacaftor 188 mg oral granules | 1 packet of lumacaftor 150 mg/ivacaftor 188 mg oral granules every other day
Moderate (Child-Pugh Class B) | 2 through 5 years | <14 kg | 1 packet of lumacaftor 100 mg/ivacaftor 125 mg oral granules | 1 packet of lumacaftor 100 mg/ivacaftor 125 mg oral granules every other day
Moderate (Child-Pugh Class B) | 2 through 5 years | ≥14 kg | 1 packet of lumacaftor 150 mg/ivacaftor 188 mg oral granules | 1 packet of lumacaftor 150 mg/ivacaftor 188 mg oral granules every other day
Moderate (Child-Pugh Class B) | 6 through 11 years | - | 2 tablets of lumacaftor 100 mg/ivacaftor 125 mg (lumacaftor 200 mg/ivacaftor 250 mg per dose) | 1 tablet of lumacaftor 100 mg/ivacaftor 125 mg
Moderate (Child-Pugh Class B) | 12 years and older | - | 2 tablets of lumacaftor 200 mg/ivacaftor 125 mg (lumacaftor 400 mg/ivacaftor 250 mg per dose) | 1 tablet of lumacaftor 200 mg/ivacaftor 125 mg
Severe (Child-Pugh Class C) | 1 through 2 years | 7 kg to <9 kg | 1 packet of lumacaftor 75 mg/ivacaftor 94 mg oral granules [or less frequently.] | N/A
Severe (Child-Pugh Class C) | 1 through 2 years | 9 kg to <14 kg | 1 packet of lumacaftor 100 mg/ivacaftor 125 mg oral granules | N/A
Severe (Child-Pugh Class C) | 1 through 2 years | ≥14 kg | 1 packet of lumacaftor 150 mg/ivacaftor 188 mg oral granules | N/A
Severe (Child-Pugh Class C) | 2 through 5 years | <14 kg | 1 packet of lumacaftor 100 mg/ivacaftor 125 mg oral granules | N/A
Severe (Child-Pugh Class C) | 2 through 5 years | ≥14 kg | 1 packet of lumacaftor 150 mg/ivacaftor 188 mg oral granules | N/A
Severe (Child-Pugh Class C) | 6 through 11 years | - | 1 tablet of lumacaftor 100 mg/ivacaftor 125 mg | 1 tablet of lumacaftor 100 mg/ivacaftor 125 mg
Severe (Child-Pugh Class C) | 12 years and older | - | 1 tablet of lumacaftor 200 mg/ivacaftor 125 mg | 1 tablet of lumacaftor 200 mg/ivacaftor 125 mg

2.3 Dosage Adjustment for Patients Taking CYP3A Inhibitors

No dosage adjustment is necessary when CYP3A inhibitors are initiated in patients already taking ORKAMBI. However, when initiating ORKAMBI in patients currently taking strong CYP3A inhibitors, reduce the ORKAMBI dosage for the first week of treatment based on age as follows [see Dosage and Administration (2.1) and Drug Interactions (7.1)]:

- 1 through 5 years of age: 1 packet of granules every other day
- 6 years of age and older: 1 tablet daily

Following this one-week period, resume the recommended daily dosage.

If ORKAMBI is interrupted for more than one-week and then re-initiated while taking strong CYP3A inhibitors, reduce the ORKAMBI dosage for the first week of treatment re-initiation based on age as follows:

- 1 through 5 years of age: 1 packet of granules every other day
- 6 years of age and older: 1 tablet daily

Following this one-week period, resume the recommended daily dosage.

3 DOSAGE FORMS AND STRENGTHS

- Tablets: 100 mg lumacaftor and 125 mg ivacaftor; supplied as pink, oval-shaped, film-coated, fixed-dose combination tablets containing 100 mg of lumacaftor and 125 mg of ivacaftor. Each tablet is printed with the characters "1V125" in black ink on one side and plain on the other.
- Tablets: 200 mg lumacaftor and 125 mg ivacaftor; supplied as pink, oval-shaped, film-coated, fixed-dose combination tablets containing 200 mg of lumacaftor and 125 mg of ivacaftor. Each tablet is printed with the characters "2V125" in black ink on one side and plain on the other.
- Oral granules: Unit-dose packets containing lumacaftor 75 mg/ivacaftor 94 mg or lumacaftor 100 mg/ivacaftor 125 mg or lumacaftor 150 mg/ivacaftor 188 mg per packet; supplied as small, white to off-white granules in unit-dose packets.

4 CONTRAINDICATIONS

None.

5 WARNINGS AND PRECAUTIONS

5.1 Use in Patients with Advanced Liver Disease

Worsening of liver function, including hepatic encephalopathy, in patients with advanced liver disease has been reported. Liver function decompensation, including liver failure leading to death, has been reported in CF patients with pre-existing cirrhosis with portal hypertension while receiving ORKAMBI. Use ORKAMBI with caution in patients with advanced liver disease and only if the benefits are expected to outweigh the risks. If ORKAMBI is used in these patients, they should be closely monitored after the initiation of treatment and the dosage should be reduced [see Dosage and Administration (2.2) and Adverse Reactions (6.1)].

5.2 Liver-related Events

Serious adverse reactions related to elevated transaminases have been reported in patients with CF receiving ORKAMBI. In some instances, these elevations have been associated with concomitant elevations in total serum bilirubin.

It is recommended that ALT, AST, and bilirubin be assessed prior to initiating ORKAMBI, every 3 months during the first year of treatment, and annually thereafter. For patients with a history of ALT, AST, or bilirubin elevations, more frequent monitoring should be considered. Patients who develop increased ALT, AST, or bilirubin should be closely monitored until the abnormalities resolve.

Dosing should be interrupted in patients with ALT or AST >5 × upper limit of normal (ULN) when not associated with elevated bilirubin. Dosing should also be interrupted in patients with ALT or AST elevations >3 × ULN when associated with bilirubin elevations >2 × ULN. Following resolution of transaminase elevations, consider the benefits and risks of resuming dosing [see Adverse Reactions (6.1)].

5.3 Hypersensitivity Reactions, Including Anaphylaxis

Hypersensitivity reactions, including cases of angioedema and anaphylaxis, have been reported in the postmarketing setting [see Adverse Reactions (6.2)]. If signs or symptoms of serious hypersensitivity reactions develop during treatment, discontinue ORKAMBI and institute appropriate therapy. Consider the benefits and risks for the individual patient to determine whether to resume treatment with ORKAMBI.

5.4 Intracranial Hypertension

Cases of intracranial hypertension (IH) have been reported in the postmarketing setting with the use of ORKAMBI [see Adverse Reactions (6.2)]. Clinical manifestations of IH include headache, blurred vision, diplopia, and potential vision loss; papilledema can be found on fundoscopy. If an unusual headache or visual disturbances occur during treatment, and IH is suspected, interrupt ORKAMBI and refer for prompt medical evaluation. Consider the benefits and risks for the individual patient to determine whether to resume treatment with ORKAMBI. Patients should be monitored until IH resolution and for recurrence. Patients with elevated vitamin A levels may be at increased risk.

5.5 Respiratory Events

Respiratory events (e.g., chest discomfort, dyspnea, and respiration abnormal) were observed more commonly in patients during initiation of ORKAMBI compared to those who received placebo. These events have led to drug discontinuation and can be serious, particularly in patients with advanced lung disease (percent predicted FEV1 <40). Clinical experience in patients with ppFEV1 <40 is limited, and additional monitoring of these patients is recommended during initiation of therapy [see Adverse Reactions (6.1)].

5.6 Effect on Blood Pressure

Increased blood pressure has been observed in some patients treated with ORKAMBI. Blood pressure should be monitored periodically in all patients being treated with ORKAMBI [see Adverse Reactions (6.1)].

5.7 Drug Interactions

Substrates of CYP3A

Lumacaftor is a strong inducer of CYP3A. Administration of ORKAMBI may decrease systemic exposure of medicinal products that are substrates of CYP3A, which may decrease therapeutic effect. Co-administration with sensitive CYP3A substrates or CYP3A substrates with a narrow therapeutic index is not recommended.

ORKAMBI may substantially decrease hormonal contraceptive exposure, reducing their effectiveness and increasing the incidence of menstruation-associated adverse reactions, e.g., amenorrhea, dysmenorrhea, menorrhagia, menstrual irregular (27% in women using hormonal contraceptives compared with 3% in women not using hormonal contraceptives). Hormonal contraceptives, including oral, injectable, transdermal, and implantable, should not be relied upon as an effective method of contraception when co-administered with ORKAMBI [see Adverse Reactions (6.1), Drug Interactions (7.3, 7.11), and Clinical Pharmacology (12.3)].

Strong CYP3A Inducers

Ivacaftor is a substrate of CYP3A4 and CYP3A5 isoenzymes. Use of ORKAMBI with strong CYP3A inducers, such as rifampin, significantly reduces ivacaftor exposure, which may reduce the therapeutic effectiveness of ORKAMBI. Therefore, co-administration with strong CYP3A inducers (e.g., rifampin, St. John's wort [Hypericum perforatum]) is not recommended [see Drug Interactions (7.2) and Clinical Pharmacology (12.3)].

5.8 Cataracts

Cases of non-congenital lens opacities have been reported in pediatric patients treated with ORKAMBI and ivacaftor, a component of ORKAMBI. Although other risk factors were present in some cases (such as corticosteroid use and exposure to radiation), a possible risk attributable to ivacaftor cannot be excluded [see Use in Specific Populations (8.4)]. Baseline and follow-up ophthalmological examinations are recommended in pediatric patients initiating ORKAMBI treatment.

6 ADVERSE REACTIONS

The following adverse reactions are discussed in greater detail in other sections of the label:

- Use in Patients with Advanced Liver Disease [see Warnings and Precautions (5.1)]
- Liver-related Events [see Warnings and Precautions (5.2)]
- Hypersensitivity Reactions, Including Anaphylaxis [see Warnings and Precautions (5.3)]
- Intracranial Hypertension [see Warnings and Precautions (5.4)]
- Respiratory Events [see Warnings and Precautions (5.5)]
- Effect on Blood Pressure [see Warnings and Precautions (5.6)]
- Cataracts [see Warnings and Precautions (5.8)]

6.1 Clinical Trials Experience

Because clinical trials are conducted under widely varying conditions, adverse reaction rates observed in the clinical trials of a drug cannot be directly compared to rates in the clinical trials of another drug and may not reflect the rates observed in practice.

The overall safety profile of ORKAMBI is based on the pooled data from 1108 patients with CF aged 12 years and older who are homozygous for the F508del mutation in the CFTR gene and who received at least one dose of study drug in two double-blind, placebo-controlled, Phase 3 clinical trials, each with 24 weeks of treatment (Trials 1 and 2).

In addition, the following clinical trials have been conducted:

- A 24-week, open-label trial (Trial 3) in 58 patients with CF aged 6 through 11 years homozygous for the F508del-CFTR mutation.
- A 24-week, placebo-controlled trial (Trial 4) in 204 patients aged 6 through 11 years homozygous for the F508del-CFTR mutation.
- A 24-week, open-label trial (Trial 5) in 46 patients aged 12 years and older homozygous for the F508del-CFTR mutation and with advanced lung disease (ppFEV1 <40).
- A 24-week, open-label trial (Trial 6) in 60 patients aged 2 through 5 years homozygous for the F508del-CFTR mutation.
- A 24-week, open-label trial (Trial 7) in 46 patients aged 1 through 2 years homozygous for the F508del-CFTR mutation.

Of the 1108 patients, in the pooled analyses of Trial 1 and Trial 2, 49% were female and 99% were Caucasian; 369 patients received ORKAMBI every 12 hours and 370 patients received placebo.

The proportion of patients who prematurely discontinued study drug due to adverse events was 5% for patients treated with ORKAMBI and 2% for patients who received placebo.

Serious adverse reactions, whether considered drug-related or not by the investigators, that occurred more frequently in patients treated with ORKAMBI included pneumonia, hemoptysis, cough, increased blood creatine phosphokinase, and transaminase elevations. These occurred in 1% or less of patients.

Table 3 shows adverse reactions occurring in ≥5% of patients with CF aged 12 years and older treated with ORKAMBI who are homozygous for the F508del mutation in the CFTR gene that also occurred at a higher rate than in patients who received placebo in the two double-blind, placebo-controlled trials.

Table 3: Incidence of Adverse Drug Reactions in ≥5% of ORKAMBI-Treated Patients Aged 12 Years and Older Who are Homozygous for the F508del Mutation in the CFTR Gene in 2 Placebo-Controlled Phase 3 Clinical Trials of 24 Weeks Duration
Adverse Reaction (Preferred Term) | ORKAMBI N=369 (%) | Placebo N=370 (%)
Dyspnea | 48 (13) | 29 (8)
Nasopharyngitis | 48 (13) | 40 (11)
Nausea | 46 (13) | 28 (8)
Diarrhea | 45 (12) | 31 (8)
Upper respiratory tract infection | 37 (10) | 20 (5)
Fatigue | 34 (9) | 29 (8)
Respiration abnormal | 32 (9) | 22 (6)
Blood creatine phosphokinase increased | 27 (7) | 20 (5)
Rash | 25 (7) | 7 (2)
Flatulence | 24 (7) | 11 (3)
Rhinorrhea | 21 (6) | 15 (4)
Influenza | 19 (5) | 8 (2)

The safety profile from two pediatric trials in CF patients aged 6 through 11 years who are homozygous for the F508del-CFTR mutation, a 24-week, open-label, multicenter safety trial in 58 patients (Trial 3) and a 24-week, placebo-controlled, clinical trial (Trial 4) in 204 patients (103 received lumacaftor 200 mg/ivacaftor 250 mg every 12 hours and 101 received placebo), was similar to that observed in Trials 1 and 2. Adverse reactions that are not listed in Table 3, and that occurred in ≥5% of lumacaftor/ivacaftor-treated patients with an incidence of ≥3% higher than placebo included: productive cough (17.5% vs 5.9%), nasal congestion (16.5% vs 7.9%), headache (12.6% vs 8.9%), abdominal pain upper (12.6% vs 6.9%), and sputum increased (10.7% vs 2.0%).

In a 24-week, open-label, multicenter, study in 60 patients aged 2 through 5 years with CF who were homozygous for the F508del-CFTR mutation (Trial 6) the safety profile was similar to that observed in studies in patients aged 6 years and older [see Clinical Pharmacology (12.2)].

In a 24-week, open-label, multicenter, study in 46 patients aged 1 through 2 years with CF who were homozygous for the F508del-CFTR mutation (Trial 7) the safety profile was similar to that observed in studies in patients aged 2 years and older [see Clinical Pharmacology (12.2)].

Additional information on selected adverse reactions from trials is detailed below:

Description of Selected Adverse Drug Reactions

Liver-related Adverse Reactions

In Trials 1 and 2, the incidence of maximum transaminase (ALT or AST) levels >8, >5, and >3 × ULN elevations were similar between patients treated with ORKAMBI and those who received placebo. Three patients who received ORKAMBI had liver-related serious adverse reactions, including two reported as transaminase elevations and one as hepatic encephalopathy, compared to none in the placebo group. Of these three, one had elevated transaminases (>3 × ULN) associated with bilirubin elevation >2 × ULN. Following discontinuation or interruption of ORKAMBI, transaminases decreased to <3 × ULN.

Among six patients with pre-existing cirrhosis and/or portal hypertension who received ORKAMBI, worsening liver function with increased ALT, AST, bilirubin, and hepatic encephalopathy was observed in one patient. The event occurred within five days of the start of dosing and resolved following discontinuation of ORKAMBI [see Warnings and Precautions (5.1, 5.2)].

During the 24-week, open-label, clinical trial in 58 patients aged 6 through 11 years (Trial 3), the incidence of maximum transaminase (ALT or AST) levels >8, >5, and >3 × ULN was 5%, 9%, and 19%. No patients had total bilirubin levels >2 × ULN. Lumacaftor/ivacaftor dosing was maintained or successfully resumed after interruption in all patients with transaminase elevations, except one patient who discontinued treatment permanently.

During the 24-week, placebo-controlled, clinical trial in 204 patients aged 6 through 11 years (Trial 4), the incidence of maximum transaminase (ALT or AST) levels >8, >5, and >3 × ULN was 1%, 5%, and 13% in the lumacaftor/ivacaftor patients, and 2%, 3%, and 8% in the placebo-treated patients. No patients had total bilirubin levels >2 × ULN. Two patients in the lumacaftor/ivacaftor group and two patients in the placebo group discontinued treatment permanently due to transaminase elevations.

During the 24-week, open-label, clinical trial in 60 patients aged 2 through 5 years (Trial 6), the incidence of maximum transaminase (ALT or AST) levels >8, >5, and >3 × ULN was 8.3% (5/60), 11.7% (7/60), and 15.0% (9/60). No patients had total bilirubin levels >2 × ULN. Three patients discontinued lumacaftor/ivacaftor treatment permanently due to transaminase elevations.

During the 24-week, open-label, clinical trial in 46 patients aged 1 through 2 years (Trial 7), the incidence of maximum transaminase (ALT or AST) levels >8, >5, and >3 × ULN was 2.2% (1/46), 4.3% (2/46), and 10.9% (5/46), respectively. No patients had total bilirubin levels >2 × ULN. One patient discontinued lumacaftor/ivacaftor treatment permanently due to transaminase elevations.

Respiratory Adverse Reactions

In Trials 1 and 2, the incidence of respiratory symptom-related adverse reactions (e.g., chest discomfort, dyspnea, and respiration abnormal) was more common in patients treated with ORKAMBI (22%) compared to patients who received placebo (14%). The incidence of these adverse reactions was more common in patients treated with ORKAMBI with lower pre-treatment FEV1. In patients treated with ORKAMBI, the majority of the events began during the first week of treatment [see Warnings and Precautions (5.5)].

During the 24-week, open-label, clinical trial in 46 patients aged 12 years and older (Trial 5) with advanced lung disease (ppFEV1 <40) [mean ppFEV1 29.1 at baseline (range: 18.3 to 42.0)], the incidence of respiratory symptom-related adverse reactions was 65% [see Warnings and Precautions (5.5)].

During the 24-week, open-label, clinical trial (Trial 3) in 58 patients aged 6 through 11 years (mean baseline ppFEV1 was 91.4), the incidence of respiratory symptom-related adverse reactions was 3% (2/58).

During the 24-week, placebo-controlled, clinical trial (Trial 4) in patients aged 6 through 11 years [mean ppFEV1 89.8 at baseline (range: 48.6 to 119.6)], the incidence of respiratory symptom-related adverse reactions was 11% in lumacaftor/ivacaftor patients and 9% in placebo patients. A decline in ppFEV1 at initiation of therapy was observed during serial post-dose spirometry assessments. The absolute change from pre-dose at 4-6 hours post-dose was -7.7 on Day 1 and -1.3 on Day 15 in lumacaftor/ivacaftor patients. The post-dose decline was resolved by Week 16.

Menstrual Abnormalities

In Trials 1 and 2, the incidence of combined menstrual abnormality adverse reactions (e.g., amenorrhea, dysmenorrhea, menorrhagia, menstrual irregular) was more common in female patients treated with ORKAMBI (10%) compared to placebo (2%). These events occurred more frequently in the subset of female patients treated with ORKAMBI who were using hormonal contraceptives (27%) compared to those not using hormonal contraceptives (3%) [see Warnings and Precautions (5.7) and Drug Interactions (7.11)].

Increased Blood Pressure

In Trials 1 and 2, adverse reactions related to increases in blood pressure (e.g., hypertension, blood pressure increased) were reported in 1.1% (4/369) of patients treated with ORKAMBI and in no patients who received placebo.

The proportion of patients who experienced a systolic blood pressure value >140 mmHg or a diastolic blood pressure >90 mmHg on at least two occasions was 3.6% and 2.2% in patients treated with ORKAMBI, respectively, compared with 1.6% and 0.5% in patients who received placebo [see Warnings and Precautions (5.6)].

6.2 Postmarketing Experience

The following adverse reactions have been identified during post approval use of ORKAMBI. Because these reactions are reported voluntarily from a population of uncertain size, it is not always possible to reliably estimate their frequency or establish a causal relationship to drug exposure.

Hepatobiliary: liver function decompensation including liver failure leading to death in patients with pre-existing cirrhosis with portal hypertension [see Warnings and Precautions (5.1)].

Immune System Disorders: anaphylaxis, angioedema

Nervous System Disorders: intracranial hypertension

7 DRUG INTERACTIONS

Potential for Other Drugs to Affect Lumacaftor/Ivacaftor

7.1 Inhibitors of CYP3A

Co-administration of lumacaftor/ivacaftor with itraconazole, a strong CYP3A inhibitor, did not impact the exposure of lumacaftor, but increased ivacaftor exposure by 4.3-fold. Due to the induction effect of lumacaftor on CYP3A, at steady-state, the net exposure of ivacaftor is not expected to exceed that when given in the absence of lumacaftor at a dose of 150 mg every 12 hours (the approved dose of ivacaftor monotherapy). Therefore, no dosage adjustment is necessary when CYP3A inhibitors are initiated in patients currently taking ORKAMBI. However, when initiating ORKAMBI in patients taking strong CYP3A inhibitors, reduce the ORKAMBI dosage as recommended for the first week of treatment to allow for the steady-state induction effect of lumacaftor. Following this period, continue with the recommended daily dose [see Dosage and Administration (2.3)].

Examples of strong CYP3A inhibitors include:

- ketoconazole, itraconazole, posaconazole, and voriconazole.
- telithromycin, clarithromycin.

No dosage adjustment is recommended when used with moderate or weak CYP3A inhibitors.

7.2 Inducers of CYP3A

Co-administration of lumacaftor/ivacaftor with rifampin, a strong CYP3A inducer, had minimal effect on the exposure of lumacaftor, but decreased ivacaftor exposure (AUC) by 57%. This may reduce the effectiveness of ORKAMBI. Therefore, co-administration with strong CYP3A inducers, such as rifampin, rifabutin, phenobarbital, carbamazepine, phenytoin, and St. John's wort (Hypericum perforatum), is not recommended [see Warnings and Precautions (5.7) and Clinical Pharmacology (12.3)].

No dosage adjustment is recommended when used with moderate or weak CYP3A inducers.

Potential for Lumacaftor/Ivacaftor to Affect Other Drugs

7.3 CYP3A Substrates

Lumacaftor is a strong inducer of CYP3A. Co-administration of lumacaftor with ivacaftor, a sensitive CYP3A substrate, decreased ivacaftor exposure by approximately 80%. Administration of ORKAMBI may decrease systemic exposure of medicinal products which are substrates of CYP3A, thereby decreasing the therapeutic effect of the medicinal product.

Co-administration of ORKAMBI is not recommended with sensitive CYP3A substrates or CYP3A substrates with a narrow therapeutic index [see Warnings and Precautions (5.7) and Clinical Pharmacology (12.3)] such as:

- Benzodiazepines: midazolam, triazolam (consider an alternative to these benzodiazepines).
- Immunosuppressants: cyclosporine, everolimus, sirolimus, and tacrolimus (avoid the use of ORKAMBI).

7.4 CYP2B6 and CYP2C Substrates

In vitro studies suggest that lumacaftor has the potential to induce CYP2B6, CYP2C8, CYP2C9, and CYP2C19; inhibition of CYP2C8 and CYP2C9 has also been observed in vitro. Additionally, in vitro studies suggest that ivacaftor may inhibit CYP2C9. Therefore, concomitant use of ORKAMBI with CYP2B6, CYP2C8, CYP2C9, and CYP2C19 substrates may alter the exposure of these substrates.

7.5 Digoxin and Other P-gp Substrates

Based on in vitro results which showed P-gp inhibition and pregnane-X-receptor (PXR) activation, lumacaftor has the potential to both inhibit and induce P-gp. Additionally, a clinical study with ivacaftor monotherapy showed that ivacaftor is a weak inhibitor of P-gp. Therefore, concomitant use of ORKAMBI with P-gp substrates may alter the exposure of these substrates.

Monitor the serum concentration of digoxin and titrate the digoxin dose to obtain the desired clinical effect.

7.6 Anti-allergics and Systemic Corticosteroids

ORKAMBI may decrease the exposure of montelukast, which may reduce its efficacy. No dosage adjustment for montelukast is recommended. Employ appropriate clinical monitoring, as is reasonable, when co-administered with ORKAMBI.

Concomitant use of ORKAMBI may reduce the exposure and effectiveness of prednisone and methylprednisolone. A higher dose of these systemic corticosteroids may be required to obtain the desired clinical effect.

7.7 Antibiotics

Concomitant use of ORKAMBI may decrease the exposure of clarithromycin, erythromycin, and telithromycin, which may reduce the effectiveness of these antibiotics. Consider an alternative to these antibiotics, such as ciprofloxacin, azithromycin, and levofloxacin.

7.8 Antifungals

Concomitant use of ORKAMBI may reduce the exposure and effectiveness of itraconazole, ketoconazole, posaconazole, and voriconazole. Concomitant use of ORKAMBI with these antifungals is not recommended. Monitor patients closely for breakthrough fungal infections if such drugs are necessary. Consider an alternative such as fluconazole.

7.9 Anti-inflammatories

Concomitant use of ORKAMBI may reduce the exposure and effectiveness of ibuprofen. A higher dose of ibuprofen may be required to obtain the desired clinical effect.

7.10 Antidepressants

Concomitant use of ORKAMBI may reduce the exposure and effectiveness of citalopram, escitalopram, and sertraline. A higher dose of these antidepressants may be required to obtain the desired clinical effect.

7.11 Hormonal Contraceptives

ORKAMBI may decrease hormonal contraceptive exposure, reducing the effectiveness. Hormonal contraceptives, including oral, injectable, transdermal, and implantable, should not be relied upon as an effective method of contraception when co-administered with ORKAMBI.

Concomitant use of ORKAMBI with hormonal contraceptives increased the menstrual abnormality events [see Adverse Reactions (6.1)]. Avoid concomitant use unless the benefit outweighs the risks.

7.12 Oral Hypoglycemics

Concomitant use of ORKAMBI may reduce the exposure and effectiveness of repaglinide and may alter the exposure of sulfonylurea. A dosage adjustment may be required to obtain the desired clinical effect. No dosage adjustment is recommended for metformin.

7.13 Proton Pump Inhibitors, H2 Blockers, Antacids

ORKAMBI may reduce the exposure and effectiveness of proton pump inhibitors such as omeprazole, esomeprazole, and lansoprazole, and may alter the exposure of ranitidine. A dose adjustment may be required to obtain the desired clinical effect. No dose adjustment is recommended for calcium carbonate antacid.

7.14 Warfarin

ORKAMBI may alter the exposure of warfarin. Monitor the international normalized ratio (INR) when warfarin co-administration with ORKAMBI is required.

7.15 Concomitant Drugs That Do Not Need Dosage Adjustment

No dosage adjustment of ORKAMBI or concomitant drug is recommended when ORKAMBI is given with the following: azithromycin, aztreonam, budesonide, ceftazidime, cetirizine, ciprofloxacin, colistimethate, colistin, dornase alfa, fluticasone, ipratropium, levofloxacin, pancreatin, pancrelipase, salbutamol, salmeterol, sulfamethoxazole, trimethoprim, tiotropium, and tobramycin. Based on the metabolism and route of elimination, ORKAMBI is not expected to impact the exposure of these drugs.

8 USE IN SPECIFIC POPULATIONS

8.1 Pregnancy

Risk Summary

There are limited and incomplete human data from clinical trials and postmarketing reports on use of ORKAMBI or its individual components, lumacaftor or ivacaftor, in pregnant women to inform a drug-associated risk. In animal reproduction studies, oral administration of lumacaftor to pregnant rats and rabbits during organogenesis demonstrated no adverse effects on fetal development at doses that produced maternal exposures up to approximately 8 (rats) and 5 (rabbits) times the exposure at the maximum recommended human dose (MRHD). Oral administration of ivacaftor to pregnant rats and rabbits during organogenesis demonstrated no adverse effects on fetal development at doses that produced maternal exposures up to approximately 7 (rats) and 45 (rabbits) times the exposure at the MRHD. No adverse developmental effects were observed after oral administration of either lumacaftor or ivacaftor to pregnant rats from organogenesis through lactation at doses that produced maternal exposures approximately 8 and 5 times the exposures at the MRHD, respectively (see Data). There are no animal reproduction studies with concomitant administration of lumacaftor and ivacaftor.

The background risk of major birth defects and miscarriage for the indicated population is unknown. In the U.S. general population, the estimated background risk of major birth defects and miscarriage in clinically recognized pregnancies is 2% to 4% and 15% to 20%, respectively.

Data

Animal Data

Lumacaftor

In an embryo-fetal development (EFD) study, pregnant rats were administered lumacaftor at oral doses of 500, 1000, or 2000 mg/kg/day during the period of organogenesis from gestation days 7-17. Lumacaftor did not affect fetal development or survival at exposures up to 8 times the MRHD (on an AUC basis at maternal oral doses up to 2000 mg/kg/day). In an EFD study, pregnant rabbits were administered lumacaftor at oral doses of 50, 100, or 200 mg/kg/day during the period of organogenesis from gestation days 7-19. Lumacaftor did not affect fetal development or survival at exposures up to 5 times the MRHD (on an AUC basis at maternal oral doses up to 200 mg/kg/day). Maternal toxicity as evidenced by decreased body weight, decreased food consumption, and clinical signs was observed at 100 and 200 mg/kg/day without any adverse fetal effects. In a pre- and post-natal development study in pregnant female rats administered lumacaftor at 250, 500, or 1000 mg/kg/day from gestation day 6 through lactation day 20, lumacaftor had no effects on delivery or growth and development of offspring at exposures up to 8 times the MRHD (on an AUC basis at maternal oral doses up to 1000 mg/kg/day). Placental transfer of lumacaftor was observed in pregnant rats and rabbits.

Ivacaftor

In an EFD study, pregnant rats were administered ivacaftor at oral doses of 50, 100, or 200 mg/kg/day during the period of organogenesis from gestation days 7-17. Ivacaftor did not affect fetal survival at exposures up to 7 times the MRHD (based on summed AUCs for ivacaftor and its metabolites at maternal oral doses up to 200 mg/kg/day). Maternal toxicity (i.e., decreased mean body weight and body weight gain) was observed at 100 and 200 mg/kg/day (5 and 7 times the exposure at the MRHD, respectively) and was associated with a decrease in fetal body weights at a maternal dose of 200 mg/kg/day (7 times the MRHD). In an EFD study, pregnant rabbits were administered ivacaftor at oral doses of 25, 50, or 100 mg/kg/day during the period of organogenesis from gestation days 7-19. Ivacaftor did not affect fetal development or survival at exposures up to 45 times the MRHD (on an ivacaftor AUC basis at maternal oral doses up to 100 mg/kg/day). Maternal toxicity (i.e., death, decreased food consumption, decreased mean body weight and body weight gain, decreased clinical condition, abortions) was observed at doses greater than or equal to 50 mg/kg/day (approximately 15 times the MRHD). In a pre- and post-natal development study, pregnant rats were administered ivacaftor at oral doses of 50, 100, or 200 mg/kg/day from gestation day 7 through lactation day 20. Ivacaftor had no effects on delivery or growth and development of offspring at exposures up to 5 times the MRHD (based on summed AUCs for ivacaftor and its metabolites at maternal oral doses up to 100 mg/kg/day). Decreased fetal body weights were observed at a maternally toxic dose that produced exposures 7 times the MRHD (based on summed AUCs for ivacaftor and its metabolites at a maternal oral dose of 200 mg/kg/day). Placental transfer of ivacaftor was observed in pregnant rats and rabbits.

8.2 Lactation

Risk Summary

There is no information regarding the presence of lumacaftor or ivacaftor in human milk, the effects on the breastfed infant, or the effects on milk production. Both lumacaftor and ivacaftor are excreted into the milk of lactating rats; however, due to species-specific differences in lactation physiology, animal lactation data may not reliably predict levels in human milk (see Data). The developmental and health benefits of breastfeeding should be considered along with the mother's clinical need for ORKAMBI and any potential adverse effects on the breastfed child from ORKAMBI or from the underlying maternal condition.

Data

Lumacaftor

Lacteal excretion of lumacaftor in rats was demonstrated following a single oral dose (100 mg/kg) of ^14C-lumacaftor administered 9 to 11 days postpartum to lactating mothers (dams). Exposure (AUC0-24h) values for lumacaftor in milk were approximately 40% of plasma levels.

Ivacaftor

Lacteal excretion of ivacaftor in rats was demonstrated following a single oral dose (100 mg/kg) of ^14C-ivacaftor administered 9 to 10 days postpartum to lactating mothers (dams). Exposure (AUC0-24h) values for ivacaftor in milk were approximately 1.5 times higher than plasma levels.

8.3 Females and Males of Reproductive Potential

ORKAMBI may decrease hormonal contraceptive exposure, reducing the effectiveness. Hormonal contraceptives, including oral, injectable, transdermal, and implantable, should not be relied upon as an effective method of contraception when co-administered with ORKAMBI [see Warnings and Precautions (5.7) and Drug Interactions (7.11)].

8.4 Pediatric Use

The safety and effectiveness of ORKAMBI in pediatric patients aged one year and older have been established. Use of ORKAMBI in these age groups is supported by evidence from adequate and well-controlled studies of ORKAMBI in patients aged 12 years and older [see Clinical Studies (14) and Adverse Reactions (6.1)] with additional data as follows:

- Extrapolation of efficacy in patients aged 12 years and older homozygous for the F508del mutation in the CFTR gene to pediatric patients aged 1 through 11 years with support from population pharmacokinetic analyses showing similar drug exposure levels in patients aged 12 years and older and in patients aged 1 through 11 years [see Clinical Pharmacology (12.3)].
- Safety data were obtained from a 24-week, open-label, clinical trial in 58 patients aged 6 through 11 years, mean age 9 years (Trial 3) and a 24-week, placebo-controlled, clinical trial in 204 patients aged 6 through 11 years (Trial 4). Trial 3 evaluated subjects with a screening ppFEV1 ≥40 [mean ppFEV1 91.4 at baseline (range: 55 to 122.7)]. Trial 4 evaluated subjects with a screening ppFEV1 ≥70 [mean ppFEV1 89.8 at baseline (range: 48.6 to 119.6)]. The safety profile of ORKAMBI in pediatric patients 6 through 11 years of age was similar to that in patients aged 12 years and older [see Adverse Reactions (6.1)]. In Trial 3, spirometry (ppFEV1) was assessed as a planned safety endpoint. The within-group LS mean absolute change from baseline in ppFEV1 at Week 24 was 2.5 percentage points. At the Week 26 safety follow-up visit (following a planned discontinuation) ppFEV1 was also assessed. The within-group LS mean absolute change in ppFEV1 from Week 24 at Week 26 was -3.2 percentage points.
- Additional safety data were obtained from Trial 6, a 24-week, open-label, clinical trial in 60 patients aged 2 through 5 years at screening (mean age at baseline 3.7 years). The safety profile in Trial 6 was similar to that in patients aged 6 years and older [see Adverse Reactions (6.1)].
- Additional safety data were obtained from Trial 7, a 24-week, open-label, clinical trial in 46 patients aged 1 to 2 years at screening (mean age at baseline 18.1 months). The safety profile in Trial 7 was similar to that in patients aged 2 years and older [see Adverse Reactions (6.1)].
- Safety was evaluated in a 96-week open-label clinical trial (Trial 8) in 52 patients (39 rolled over from Trial 7 and 13 ORKAMBI naïve) aged 1 to 2 years. Adverse reactions from trial 8 were generally similar to those reported in Trial 7.

The safety and effectiveness of ORKAMBI in patients with CF younger than 1 year of age have not been established.

Cases of non-congenital lens opacities have been reported in pediatric patients treated with ORKAMBI and ivacaftor, a component of ORKAMBI. Although other risk factors were present in some cases (such as corticosteroid use and exposure to radiation), a possible risk attributable to ivacaftor cannot be excluded [see Warnings and Precautions (5.8)].

Juvenile Animal Toxicity Data

In a juvenile toxicology study in which ivacaftor was administered to rats from post-natal days 7 to 35, cataracts were observed at all dose levels, ranging from 0.3 to 2 times the MRHD (based on summed AUCs for ivacaftor and its metabolites at oral doses of 10-50 mg/kg/day). This finding has not been observed in older animals.

8.5 Geriatric Use

CF is largely a disease of children and young adults. Clinical trials of ORKAMBI did not include sufficient numbers of patients 65 years of age and over to determine whether they respond differently from younger patients.

8.6 Hepatic Impairment

No dosage adjustment is necessary for patients with mild hepatic impairment (Child-Pugh Class A). A dose reduction to 2 tablets in the morning and 1 tablet in the evening is recommended for patients aged 6 years and older with moderate hepatic impairment (Child-Pugh Class B). A dose reduction to 1 packet of oral granules in the morning daily and 1 packet of oral granules in the evening every other day is recommended for patients aged 1 to 5 years old with moderate hepatic impairment (Child-Pugh Class B).

Studies have not been conducted in patients with severe hepatic impairment (Child-Pugh Class C), but exposure is expected to be higher than in patients with moderate hepatic impairment. Therefore, use with caution at a maximum dose of 1 tablet in the morning and 1 tablet in the evening or less frequently, or 1 packet of oral granules once daily or less frequently in patients with severe hepatic impairment after weighing the risks and benefits of treatment [see Warnings and Precautions (5.1), Adverse Reactions (6.1), Clinical Pharmacology (12.3), and Patient Counseling Information (17)].

8.7 Renal Impairment

ORKAMBI has not been studied in patients with mild, moderate, or severe renal impairment or in patients with end-stage renal disease. No dosage adjustment is necessary for patients with mild to moderate renal impairment. Caution is recommended while using ORKAMBI in patients with severe renal impairment (creatinine clearance ≤30 mL/min) or end-stage renal disease.

8.8 Patients with Severe Lung Dysfunction

The Phase 3 trials (Trials 1 and 2 [see Clinical Studies (14)]) included 29 patients receiving ORKAMBI with ppFEV1 <40 at baseline. The treatment effect in this subgroup was comparable to that observed in patients with ppFEV1 ≥40.

8.9 Patients After Organ Transplantation

ORKAMBI has not been studied in patients with CF who have undergone organ transplantation. Use in transplanted patients is not recommended due to potential drug-drug interactions [see Drug Interactions (7.3)].

10 OVERDOSAGE

There have been no reports of overdose with ORKAMBI.

The highest repeated dose was lumacaftor 1000 mg once daily/ivacaftor 450 mg q12h administered to 49 healthy subjects for 7 days in a trial evaluating the effect of ORKAMBI on electrocardiograms (ECGs). Adverse events reported at an increased incidence of ≥5% compared to the lumacaftor 600 mg/ivacaftor 250 mg dosing period and placebo included: headache (29%), transaminase increased (18%), and generalized rash (10%).

No specific antidote is available for overdose with ORKAMBI. Treatment of overdose consists of general supportive measures including monitoring of vital signs and observation of the clinical status of the patient.

11 DESCRIPTION

The active ingredients in ORKAMBI tablets are lumacaftor, which has the following chemical name: 3-[6-({[1-(2,2-difluoro-1,3-benzodioxol-5-yl)cyclopropyl]carbonyl}amino)-3-methylpyridin-2-yl]benzoic acid, and ivacaftor, a CFTR potentiator, which has the following chemical name: N-(2,4-di-tert-butyl-5-hydroxyphenyl)-1,4-dihydro-4-oxoquinoline-3-carboxamide. The molecular formula for lumacaftor is C24H18F2N2O5 and for ivacaftor is C24H28N2O3. The molecular weights for lumacaftor and ivacaftor are 452.41 and 392.49, respectively. The structural formulas are:

lumacaftor
ivacaftor

Lumacaftor is a white to off-white powder that is practically insoluble in water (0.02 mg/mL). Ivacaftor is a white to off-white powder that is practically insoluble in water (<0.05 µg/mL).

ORKAMBI is available as a pink, oval-shaped, film-coated tablet for oral administration containing 200 mg of lumacaftor and 125 mg of ivacaftor. Each ORKAMBI tablet contains 200 mg of lumacaftor and 125 mg of ivacaftor, and the following inactive ingredients: cellulose, microcrystalline; croscarmellose sodium; hypromellose acetate succinate; magnesium stearate; povidone; and sodium lauryl sulfate. The tablet film coat contains carmine, FD&C Blue #1, FD&C Blue #2, polyethylene glycol, polyvinyl alcohol, talc, and titanium dioxide. The printing ink contains ammonium hydroxide, iron oxide black, propylene glycol, and shellac.

ORKAMBI is also available as a pink, oval-shaped, film-coated tablet for oral administration containing 100 mg of lumacaftor and 125 mg of ivacaftor. Each ORKAMBI tablet contains 100 mg of lumacaftor and 125 mg of ivacaftor, and the following inactive ingredients: cellulose, microcrystalline; croscarmellose sodium; hypromellose acetate succinate; magnesium stearate; povidone; and sodium lauryl sulfate. The tablet film coat contains carmine, FD&C Blue #1, FD&C Blue #2, polyethylene glycol, polyvinyl alcohol, talc, and titanium dioxide. The printing ink contains ammonium hydroxide, iron oxide black, propylene glycol, and shellac.

ORKAMBI is also available as white to off-white granules for oral administration and enclosed in a unit-dose packet containing lumacaftor 75 mg/ivacaftor 94 mg, lumacaftor 100 mg/ivacaftor 125 mg or lumacaftor 150 mg/ivacaftor 188 mg per packet. Each unit-dose packet of ORKAMBI oral granules contains lumacaftor 75 mg/ivacaftor 94 mg, lumacaftor 100 mg/ivacaftor 125 mg or lumacaftor 150 mg/ivacaftor 188 mg per packet and the following inactive ingredients: cellulose, microcrystalline; croscarmellose sodium; hypromellose acetate succinate; povidone; and sodium lauryl sulfate.

12 CLINICAL PHARMACOLOGY

12.1 Mechanism of Action

The CFTR protein is a chloride channel present at the surface of epithelial cells in multiple organs. The F508del mutation results in protein misfolding, causing a defect in cellular processing and trafficking that targets the protein for degradation and therefore reduces the quantity of CFTR at the cell surface. The small amount of F508del-CFTR that reaches the cell surface is less stable and has low channel-open probability (defective gating activity) compared to wild-type CFTR protein.

Lumacaftor improves the conformational stability of F508del-CFTR, resulting in increased processing and trafficking of mature protein to the cell surface. Ivacaftor is a CFTR potentiator that facilitates increased chloride transport by potentiating the channel-open probability (or gating) of the CFTR protein at the cell surface. In vitro studies have demonstrated that both lumacaftor and ivacaftor act directly on the CFTR protein in primary human bronchial epithelial cultures and other cell lines harboring the F508del-CFTR mutation to increase the quantity, stability, and function of F508del-CFTR at the cell surface, resulting in increased chloride ion transport. In vitro responses do not necessarily correspond to in vivo pharmacodynamic response or clinical benefit.

12.2 Pharmacodynamics

Sweat Chloride Evaluation

Changes in sweat chloride in response to relevant doses of lumacaftor alone or in combination with ivacaftor were evaluated in a double-blind, placebo-controlled, Phase 2 clinical trial in patients with CF aged 18 years and older either homozygous or heterozygous for the F508del mutation. In that trial, 10 patients (homozygous for F508del) completed dosing with lumacaftor alone 400 mg q12h for 28 days followed by the addition of ivacaftor 250 mg q12h for an additional 28 days and 25 patients (homozygous or heterozygous for F508del) completed dosing with placebo. The treatment difference between lumacaftor 400 mg q12h alone and placebo evaluated as mean change in sweat chloride from baseline to Day 28 compared to placebo was -8.2 mmol/L (95% CI: -14, -2). The treatment difference between the combination of lumacaftor 400 mg/ivacaftor 250 mg q12h and placebo evaluated as mean change in sweat chloride from baseline to Day 56 compared to placebo was -11 mmol/L (95% CI: -18, -4).

Changes in sweat chloride in response to lumacaftor/ivacaftor were also evaluated in a 24-week, open-label, clinical trial (Trial 3) in 58 patients with CF, aged 6 through 11 years (homozygous for F508del) who received lumacaftor 200 mg/ivacaftor 250 mg q12h for 24 weeks. Patients treated with lumacaftor/ivacaftor had a reduction in sweat chloride at Day 15 that was sustained through Week 24. The within-group LS mean absolute change from baseline in sweat chloride was -20.4 mmol/L at Day 15 and -24.8 mmol/L at Week 24. In addition, sweat chloride was also assessed after a 2-week washout period to evaluate the off-drug response. The within-group LS mean absolute change in sweat chloride from Week 24 at Week 26 following the 2-week washout period was 21.3 mmol/L.

Changes in sweat chloride in response to lumacaftor/ivacaftor were also evaluated in a 24-week, open-label, clinical trial (Trial 6) in 60 patients with CF, aged 2 through 5 years (homozygous for F508del) who received either lumacaftor 100 mg/ivacaftor 125 mg every 12 hours or lumacaftor 150 mg/ivacaftor 188 mg every 12 hours for 24 weeks. Treatment with lumacaftor/ivacaftor demonstrated a reduction in sweat chloride at Week 4 that was sustained through Week 24. The mean absolute change from baseline in sweat chloride was –31.7 mmol/L (95% CI: -35.7, -27.6) at Week 24. In addition, sweat chloride was also assessed after a 2-week washout period to evaluate the off-drug response. The mean absolute change in sweat chloride from Week 24 at Week 26 following the 2-week washout period was an increase of 33.0 mmol/L (95% CI: 28.9, 37.1; P<0.0001).

Changes in sweat chloride in response to lumacaftor/ivacaftor were evaluated in a 24-week, open-label, clinical trial (Trial 7) in 46 patients with CF, aged 1 through 2 years (homozygous for F508del) who received lumacaftor 75 mg/ivacaftor 94 mg (patient weighing 7 kg to <9 kg at screening), lumacaftor 100 mg/ivacaftor 125 mg (patient weighing 9 kg to <14 kg at screening), lumacaftor 150 mg/ivacaftor 188 mg (patient weighing ≥14 kg at screening), every 12 hours for 24 weeks. Treatment with lumacaftor/ivacaftor demonstrated a reduction in sweat chloride at Week 4 which was sustained through Week 24. The mean absolute change from baseline in sweat chloride at Week 24 was -29.1 mmol/L (95% CI: -34.8, -23.4). In addition, sweat chloride was also assessed after a 2-week washout period to evaluate the off-drug response. The mean absolute change in sweat chloride from Week 24 at Week 26 following the 2-week washout period was 27.3 mmol/L (95% CI: 22.3, 32.3).

There was no direct correlation between decrease in sweat chloride levels and improvement in lung function (ppFEV1).

Cardiac Electrophysiology

The effect of multiple doses of lumacaftor 600 mg once daily/ivacaftor 250 mg q12h and lumacaftor 1000 mg once daily/ivacaftor 450 mg q12h on QTc interval was evaluated in a randomized, placebo- and active-controlled (400 mg moxifloxacin), parallel, thorough QT study in 168 healthy subjects. No meaningful changes in QTc interval were observed with either lumacaftor 600 mg once daily/ivacaftor 250 mg q12h and lumacaftor 1000 mg once daily/ivacaftor 450 mg q12h dose groups. A maximum decrease in mean heart rate of up to 8 beats per minute (bpm) from baseline was observed with lumacaftor/ivacaftor treatment. In Trials 1 and 2, a similar decrease in heart rate was observed in patients during initiation of ORKAMBI (lumacaftor 400 mg/ivacaftor 250 mg q12h).

12.3 Pharmacokinetics

The exposure (AUC) of lumacaftor is approximately 2-fold higher in healthy adult volunteers compared to exposure in patients with CF. The exposure of ivacaftor is similar between healthy adult volunteers and patients with CF. After twice daily dosing, steady-state plasma concentrations of lumacaftor and ivacaftor in healthy subjects were generally reached after approximately 7 days of treatment, with an accumulation ratio of approximately 1.9 for lumacaftor. The steady-state exposure of ivacaftor is lower than that of Day 1 due to the CYP3A induction effect of lumacaftor.

Table 4: Mean (SD) Pharmacokinetic Parameters of Lumacaftor and Ivacaftor at Steady-State in Subjects with CF
 | Drug | Cmax (μg/mL) | t½ [Based on lumacaftor 200 mg q12h/ivacaftor 250 mg q12h studied in healthy subjects.] (h) | AUC0-12h (μg∙h/mL)
Lumacaftor 400 mg q12h/ Ivacaftor 250 mg q12h | Lumacaftor | 25.0 (7.96) | 25.2 (9.94) | 198 (64.8)
Lumacaftor 400 mg q12h/ Ivacaftor 250 mg q12h | Ivacaftor | 0.602 (0.304) | 9.34 (3.81) | 3.66 (2.25)

Absorption

When a single dose of lumacaftor/ivacaftor was administered with fat-containing foods, lumacaftor exposure was approximately 2 times higher and ivacaftor exposure was approximately 3 times higher than when taken in a fasting state.

Following multiple oral dose administration of lumacaftor in combination with ivacaftor, the exposure of lumacaftor generally increased proportional to dose over the range of 200 mg every 24 hours to 400 mg every 12 hours. The median (range) tmax of lumacaftor is approximately 4.0 hours (2.0; 9.0) in the fed state.

Following multiple oral dose administration of ivacaftor in combination with lumacaftor, the exposure of ivacaftor generally increased with dose from 150 mg every 12 hours to 250 mg every 12 hours. The median (range) tmax of ivacaftor is approximately 4.0 hours (2.0; 6.0) in the fed state.

Distribution

Lumacaftor is approximately 99% bound to plasma proteins, primarily to albumin. After oral administration of 200 mg every 24 hours for 28 days to patients with CF in a fed state, the mean (±SD) for apparent volumes of distribution was 86.0 (69.8) L.

Ivacaftor is approximately 99% bound to plasma proteins, primarily to alpha 1-acid glycoprotein and albumin.

Elimination

The half-life of lumacaftor is approximately 26 hours in patients with CF. The typical apparent clearance, CL/F (CV), of lumacaftor was estimated to be 2.38 L/hr (29.4%) for patients with CF. The half-life of ivacaftor when given with lumacaftor is approximately 9 hours in healthy subjects. The typical CL/F (CV), of ivacaftor when given in combination with lumacaftor was estimated to be 25.1 L/hr (40.5%) for patients with CF.

Metabolism

Lumacaftor is not extensively metabolized in humans with the majority of lumacaftor excreted unchanged in the feces. In vitro and in vivo data indicate that lumacaftor is mainly metabolized via oxidation and glucuronidation.

Ivacaftor is extensively metabolized in humans. In vitro and in vivo data indicate that ivacaftor is primarily metabolized by CYP3A. M1 and M6 are the two major metabolites of ivacaftor in humans.

Excretion

Following oral administration of lumacaftor, the majority of lumacaftor (51%) is excreted unchanged in the feces. There was minimal elimination of lumacaftor and its metabolites in urine (only 8.6% of total radioactivity was recovered in the urine with 0.18% as unchanged parent).

Following oral administration of ivacaftor alone, the majority of ivacaftor (87.8%) is eliminated in the feces after metabolic conversion. There was minimal elimination of ivacaftor and its metabolites in urine (only 6.6% of total radioactivity was recovered in the urine).

Specific Populations

Pediatric Patients

The following conclusions about exposures between adults and the pediatric population are based on population pharmacokinetics (PK) analyses:

Table 5: Mean (SD) Lumacaftor and Ivacaftor Exposure by Age Group
Age Group | Weight | Dose | Mean Lumacaftor (SD) [The mean lumacaftor (SD) AUCss is comparable to the mean AUCss in patients aged 12 years and older administered ORKAMBI tablets.] AUCss (µg∙h/mL) | Mean Ivacaftor (SD) [The mean ivacaftor (SD) AUCss is comparable to the mean AUCss in patients aged 12 years and older administered ORKAMBI tablets.] AUCss (µg∙h/mL)
Patients aged 1 to <2 years | 7 kg to <9 kg | lumacaftor 75 mg/ivacaftor 94 mg every 12 hours. | 234 | 7.98
Patients aged 1 to <2 years | 9 kg to <14 kg | lumacaftor 100 mg/ivacaftor 125 mg every 12 hours. | 191 (40.6) | 5.35 (1.61)
Patients aged 1 to <2 years | ≥14 kg | lumacaftor 150 mg/ivacaftor 188 mg every 12 hours. | 116 | 5.82
Patients aged 2 through 5 years | <14 kg | lumacaftor 100 mg/ivacaftor 125 mg every 12 hours. | 180 (45.5) | 5.92 (4.61)
Patients aged 2 through 5 years | ≥14 kg | lumacaftor 150 mg/ivacaftor 188 mg every 12 hours. | 217 (48.6) | 5.90 (1.93)
Patients aged 6 through 11 years | - | lumacaftor 200 mg/ivacaftor 250 mg every 12 hours. | 203 (57.4) | 5.26 (3.08)
Patients aged 12 to <18 years | - | lumacaftor 400 mg/ivacaftor 250 mg every 12 hours. | 241 (61.4) | 3.90 (1.56)

Male and Female Patients

The pharmacokinetics of ORKAMBI was evaluated using a population PK analyses of data from clinical studies of lumacaftor given in combination with ivacaftor. Results indicate no clinically relevant difference in pharmacokinetic parameters for lumacaftor and ivacaftor between males and females.

Patients with Renal Impairment

Pharmacokinetic studies have not been performed with ORKAMBI in patients with renal impairment [see Use in Specific Populations (8.7)].

Patients with Hepatic Impairment

Following multiple doses of lumacaftor/ivacaftor for 10 days, subjects with moderately impaired hepatic function (Child-Pugh Class B, score 7 to 9) had approximately 50% higher exposures (AUC0-12h) and approximately 30% higher Cmax for both lumacaftor and ivacaftor compared with healthy subjects matched for demographics.

Pharmacokinetic studies have not been conducted in patients with mild (Child-Pugh Class A, score 5 to 6) or severe hepatic impairment (Child-Pugh Class C, score 10 to 15) receiving ORKAMBI [see Dosage and Administration (2.2), Warnings and Precautions (5.1), Adverse Reactions (6), and Use in Specific Populations (8.6)].

Drug Interaction Studies

Drug interaction studies were performed with lumacaftor/ivacaftor and other drugs likely to be co-administered or drugs commonly used as probes for pharmacokinetic interaction studies [see Drug Interactions (7)].

Potential for Lumacaftor/Ivacaftor to Affect Other Drugs

Lumacaftor is a strong inducer of CYP3A. Co-administration of lumacaftor with ivacaftor, a sensitive CYP3A substrate, decreased ivacaftor exposure by 80%. Ivacaftor is a weak inhibitor of CYP3A when given as monotherapy. The net effect of lumacaftor/ivacaftor therapy is strong CYP3A induction [see Drug Interactions (7.3)].

Based on in vitro results which showed P-gp inhibition and PXR activation, lumacaftor has the potential to both inhibit and induce P-gp. A clinical study with ivacaftor monotherapy showed that ivacaftor is a weak inhibitor of P-gp. Therefore, concomitant use of ORKAMBI with P-gp substrates may alter the exposure of these substrates [see Drug Interactions (7.5)].

In vitro studies suggest that lumacaftor has the potential to induce CYP2B6, CYP2C8, CYP2C9, and CYP2C19; inhibition of CYP2C8 and CYP2C9 has also been observed in vitro. In vitro studies suggest that ivacaftor may inhibit CYP2C9. Therefore, concomitant use of ORKAMBI with CYP2B6, CYP2C8, CYP2C9, and CYP2C19 substrates may alter the exposure of these substrates [see Drug Interactions (7.4)].

Potential for Other Drugs to Affect Lumacaftor/Ivacaftor

Lumacaftor exposure is not affected by concomitant CYP3A inducers or inhibitors. Exposure of ivacaftor when given in combination with lumacaftor is reduced by concomitant CYP3A inducers and increased by concomitant CYP3A inhibitors [see Dosage and Administration (2.3), Warnings and Precautions (5.7), and Drug Interactions (7)].

The effects of co-administered drugs on the exposure of lumacaftor and ivacaftor are shown in Table 6 [see Dosage and Administration (2.3), Warnings and Precautions (5.7), and Drug Interactions (7)].

Table 6: Impact of Other Drugs on Lumacaftor 200 mg q12h/Ivacaftor 250 mg q12h
Co-administered Drug | Dose of Co-administered Drug | Effect on PK [↑ = increase, ↓ = decrease, ↔ = no change.] | Mean Ratio (90% CI) of Lumacaftor and Ivacaftor No Effect=1.0
Co-administered Drug | Dose of Co-administered Drug | Effect on PK [↑ = increase, ↓ = decrease, ↔ = no change.] | AUC | Cmax
CYP3A inhibitor: itraconazole | 200 mg once daily | ↔ Lumacaftor | 0.97 (0.91, 1.02) | 0.99 (0.92, 1.05)
CYP3A inhibitor: itraconazole | 200 mg once daily | ↑ Ivacaftor | 4.30 [The net exposure of ivacaftor is not expected to exceed that when given in the absence of lumacaftor at a dose of 150 mg every 12 hours, the approved dose of ivacaftor monotherapy.] (3.78, 4.88) | 3.64 (3.19, 4.17)
CYP3A inducer: rifampin | 600 mg once daily | ↔ Lumacaftor | 0.87 (0.81, 0.93) | 0.96 (0.87, 1.05)
CYP3A inducer: rifampin | 600 mg once daily | ↓ Ivacaftor | 0.43 (0.38, 0.49) | 0.50 (0.43, 0.58)
Other: ciprofloxacin | 750 mg q12h | ↔ Lumacaftor | 0.86 (0.79, 0.95) | 0.88 (0.80, 0.97)
Other: ciprofloxacin | 750 mg q12h | ↔ Ivacaftor | 1.29 (1.12, 1.48) | 1.29 (1.11, 1.49)
CI = Confidence Interval; PK = Pharmacokinetics.

13 NONCLINICAL TOXICOLOGY

13.1 Carcinogenesis, Mutagenesis, Impairment of Fertility

No studies of carcinogenicity, mutagenicity, or impairment of fertility were conducted with ORKAMBI; however, studies are available for individual components, lumacaftor and ivacaftor, as described below.

Lumacaftor

A two-year study in Sprague-Dawley rats and a 26-week study in transgenic Tg.rasH2 mice were conducted to assess carcinogenic potential of lumacaftor. No evidence of tumorigenicity was observed in rats at lumacaftor oral doses up to 1000 mg/kg/day (approximately 5 and 13 times the MRHD on a lumacaftor AUC basis in males and females, respectively). No evidence of tumorigenicity was observed in Tg.rasH2 mice at lumacaftor oral doses up to 1500 and 2000 mg/kg/day in female and male mice, respectively. Lumacaftor was negative for genotoxicity in the following assays: Ames test for bacterial gene mutation, in vitro chromosomal aberration assay in Chinese hamster ovary cells, and in vivo mouse micronucleus test.

Lumacaftor had no effects on fertility and reproductive performance indices in male and female rats at an oral dose of 1000 mg/kg/day (approximately 3 and 8 times, respectively, the MRHD on a lumacaftor AUC basis).

Ivacaftor

Two-year studies were conducted in mice and rats to assess carcinogenic potential of ivacaftor. No evidence of tumorigenicity was observed in mice and rats at ivacaftor oral doses up to 200 mg/kg/day and 50 mg/kg/day, respectively (approximately equivalent to 3 and 10 times the MRHD based on summed AUCs of ivacaftor and its metabolites).

Ivacaftor was negative for genotoxicity in the following assays: Ames test for bacterial gene mutation, in vitro chromosomal aberration assay in Chinese hamster ovary cells, and in vivo mouse micronucleus test.

Ivacaftor impaired fertility and reproductive performance indices in male and female rats at an oral dose of 200 mg/kg/day (approximately 15 and 7 times the MRHD based on summed AUCs of ivacaftor and its metabolites). Increases in prolonged diestrus were observed in females at 200 mg/kg/day. Ivacaftor also increased the number of females with all nonviable embryos and decreased corpora lutea, implantations, and viable embryos in rats at 200 mg/kg/day (approximately 7 times the MRHD based on summed AUCs of ivacaftor and its metabolites) when dams were dosed prior to and during early pregnancy. These impairments of fertility and reproductive performance in male and female rats at 200 mg/kg/day were attributed to severe toxicity. No effects on male or female fertility and reproductive performance indices were observed at an oral dose of ≤100 mg/kg/day (approximately 8 and 5 times the MRHD based on summed AUCs of ivacaftor and its metabolites).

14 CLINICAL STUDIES

Dose Ranging

Dose ranging for the clinical program consisted primarily of one double-blind, placebo-controlled, multiple-cohort trial which included 97 Caucasian patients with CF (homozygous for the F508del mutation) aged 18 years and older with a screening ppFEV1 ≥40. In the trial, 76 patients (homozygous for the F508del mutation) were randomized to receive lumacaftor alone at once daily doses of 200 mg, 400 mg, or 600 mg or 400 mg q12h for 28 days followed by the addition of ivacaftor 250 mg q12h and 27 patients (homozygous or heterozygous for the F508del mutation) received placebo. During the initial 28-day lumacaftor monotherapy period, treatment with lumacaftor demonstrated a dose-dependent decrease in ppFEV1 compared to placebo. Changes from Day 1 at Day 28 in ppFEV1 compared to placebo were 0.24, -1.4, -2.7, and -4.6 for the 200 mg once daily, 400 mg once daily, 600 mg once daily, and 400 mg q12h lumacaftor doses, respectively. Following the addition of ivacaftor 250 mg q12h, the changes from Day 1 at Day 56 in ppFEV1 compared to placebo were 3.8, 2.7, 5.6, and 4.2, respectively.

Sweat chloride was also assessed in this trial. Following the initial 28 days of lumacaftor monotherapy, the changes from Day 1 at Day 28 in sweat chloride compared to placebo were -4.9, -8.3, -6.1, and -8.2 mmol/L for the 200 mg once daily, 400 mg once daily, 600 mg once daily, and 400 mg q12h lumacaftor doses, respectively. Following the addition of ivacaftor 250 mg q12h, the changes from Day 1 at Day 56 in sweat chloride compared to placebo were -5.0, -9.8, -9.5, and -11 mmol/L, respectively.

These data supported the evaluation of lumacaftor 400 mg/ivacaftor 250 mg q12h (ORKAMBI) and lumacaftor 600 mg once daily/ivacaftor 250 mg q12h in the confirmatory trials.

Confirmatory

The efficacy of ORKAMBI in patients with CF who are homozygous for the F508del mutation in the CFTR gene was evaluated in two randomized, double-blind, placebo-controlled, 24-week clinical trials (Trials 1 and 2) in 1108 clinically stable patients with CF of whom 369 patients received ORKAMBI twice daily.

Trial 1 evaluated 549 patients with CF who were aged 12 years and older (mean age 25.1 years) with ppFEV1 at screening between 40-90 [mean ppFEV1 60.7 at baseline (range: 31.1 to 94.0)]. Trial 2 evaluated 559 patients aged 12 years and older (mean age 25.0 years) with ppFEV1 at screening between 40-90 [mean ppFEV1 60.5 at baseline (range: 31.3 to 99.8)]. Patients with a history of colonization with organisms such as Burkholderia cenocepacia, Burkholderia dolosa, or Mycobacterium abscessus, or who had 3 or more abnormal liver function tests (ALT, AST, AP, GGT ≥3 × the ULN or total bilirubin ≥2 × the ULN) were excluded.

Patients in both trials were randomized 1:1:1 to receive either ORKAMBI (lumacaftor 400 mg q12h/ivacaftor 250 mg q12h; or lumacaftor 600 mg once daily/ivacaftor 250 mg q12h) or placebo. Patients took the study drug with fat-containing food for 24 weeks in addition to their prescribed CF therapies (e.g., bronchodilators, inhaled antibiotics, dornase alfa, and hypertonic saline).

The primary efficacy endpoint in both trials was change in lung function as determined by absolute change from baseline in ppFEV1 at Week 24, assessed as the average of the treatment effects at Week 16 and at Week 24. In both trials, treatment with ORKAMBI resulted in a statistically significant improvement in ppFEV1. The treatment difference between ORKAMBI and placebo for the mean absolute change in ppFEV1 from baseline at Week 24 (assessed as the average of the treatment effects at Week 16 and at Week 24) was 2.6 percentage points [95% CI (1.2, 4.0)] in Trial 1 (P=0.0003) and 3.0 percentage points [95% CI (1.6, 4.4)] in Trial 2 (P<0.0001). These changes persisted throughout the 24-week treatment period (see Figure 1). Improvements in ppFEV1 were observed regardless of age, disease severity, sex, and geographic region.

Figure 1. Absolute Change From Baseline at Each Visit in Percent Predicted FEV1 in Trial 1 and Trial 2.

LS = Least Squares; q12h = every 12 hours

Key secondary efficacy variables included relative change from baseline in ppFEV1 at Week 24, assessed as the average of the treatment effects at Week 16 and at Week 24; absolute change from baseline in BMI at Week 24; absolute change from baseline in Cystic Fibrosis Questionnaire-Revised (CFQ-R) Respiratory Domain score at Week 24, a measure of respiratory symptoms relevant to patients with CF such as cough, sputum production, and difficulty breathing; proportion of patients achieving ≥5% relative change from baseline in ppFEV1 using the average of Week 16 and Week 24; and number of pulmonary exacerbations through Week 24. For the purposes of these trials, a pulmonary exacerbation was defined as a change in antibiotic therapy (IV, inhaled, or oral) as a result of 4 or more of 12 pre-specified sino-pulmonary signs/symptoms.

Table 7: Summary of Other Efficacy Endpoints in Trials 1 and 2 [In each trial, a hierarchical testing procedure was performed within each active treatment arm for primary and secondary endpoints vs. placebo; at each step, P≤0.0250 and all previous tests also meeting this level of significance was required for statistical significance.]
 |  | Trial 1 |  | Trial 2
 |  | Placebo (n=184) | ORKAMBI LUM 400 mg q12h/IVA 250 mg q12h (n=182) | Placebo (n=187) | ORKAMBI LUM 400 mg q12h/IVA 250 mg q12h (n=187)
Relative change in ppFEV 1 at Week 24 [Assessed as the average of the treatment effects at Week 16 and Week 24.] (%) | Treatment difference (95% CI) | – | 4.3 (1.9, 6.8) P=0.0006 [Indicates statistical significance confirmed in the hierarchical testing procedure. Other efficacy measures considered not statistically significant.] | – | 5.3 (2.7, 7.8) P<0.0001
Absolute change in BMI at Week 24 (kg/m^2) | Treatment difference (95% CI) | – | 0.1 (-0.1, 0.3) | – | 0.4 (0.2, 0.5) P=0.0001
Absolute change in CFQ-R Respiratory Domain Score (Points) at Week 24 | Treatment difference (95% CI) | – | 1.5 (-1.7, 4.7) | – | 2.9 (-0.3, 6.0)
Proportion of patients with ≥5% relative change in ppFEV 1 at Week 24 | % | 22% | 37% | 23% | 41%
Proportion of patients with ≥5% relative change in ppFEV 1 at Week 24 | Odds ratio (95% CI) | – | 2.1 (1.3, 3.3) | – | 2.4 (1.5, 3.7)
Number of pulmonary exacerbations through Week 24 | # of events (rate per 48 weeks) | 112 (1.1) | 73 (0.7) | 139 (1.2) | 79 (0.7)
Number of pulmonary exacerbations through Week 24 | Rate ratio (95% CI) | – | 0.7 (0.5, 0.9) | – | 0.6 (0.4, 0.8)

16 HOW SUPPLIED/STORAGE AND HANDLING

ORKAMBI (lumacaftor 200 mg/ivacaftor 125 mg) is supplied as pink, oval-shaped tablets; each tablet contains 200 mg of lumacaftor and 125 mg of ivacaftor, printed with "2V125" in black ink on one side and plain on the other, and is packaged as follows:

112–count tablet box containing a 4-week supply (4 weekly cartons of 7 daily blister strips with 4 tablets per strip). | NDC 51167-809-01

ORKAMBI (lumacaftor 100 mg/ivacaftor 125 mg) is supplied as pink, oval-shaped tablets; each tablet contains 100 mg of lumacaftor and 125 mg of ivacaftor, printed with "1V125" in black ink on one side and plain on the other, and is packaged as follows:

112–count tablet box containing a 4-week supply (4 weekly cartons of 7 daily blister strips with 4 tablets per strip). | NDC 51167-700-02

ORKAMBI (lumacaftor/ivacaftor) oral granules are supplied as small white to off-white granules and enclosed in unit-dose packets as follows:

56-count carton (contains 56 unit-dose packets of lumacaftor 75 mg/ivacaftor 94 mg per packet) | NDC 51167-122-01
56-count carton (contains 56 unit-dose packets of lumacaftor 100 mg/ivacaftor 125 mg per packet) | NDC 51167-900-01
56-count carton (contains 56 unit-dose packets of lumacaftor 150 mg/ivacaftor 188 mg per packet) | NDC 51167-500-02

STORAGE AND HANDLING

Store at 20°C - 25°C (68°F - 77°F); excursions permitted to 15°C - 30°C (59°F - 86°F) [see USP Controlled Room Temperature].

17 PATIENT COUNSELING INFORMATION

Advise the patient to read the FDA-approved patient labeling (Patient Information).

Advanced Liver Disease

Inform patients that worsening of liver function, including hepatic encephalopathy, in patients with advanced liver disease occurred in some patients treated with ORKAMBI. Liver function decompensation, including liver failure leading to death, has been reported in CF patients with pre-existing cirrhosis with portal hypertension while receiving ORKAMBI [see Warnings and Precautions (5.1)].

Abnormalities in Liver Function and Testing

Inform patients that abnormalities in liver function have occurred in patients treated with ORKAMBI. Blood tests to measure transaminases (ALT and AST) and bilirubin will be performed prior to initiating ORKAMBI, every 3 months during the first year of therapy, and annually thereafter. Advise patients to contact their healthcare provider if they develop symptoms consistent with hepatotoxicity [see Warnings and Precautions (5.2)].

Hypersensitivity Reactions, Including Anaphylaxis

Hypersensitivity reactions including angioedema and anaphylaxis are possible with use of ORKAMBI. Inform patients of the early signs of hypersensitivity reactions including rash, hives, itching, facial swelling, tightness of the chest and wheezing. Advise patients to discontinue use of ORKAMBI immediately and contact their physician or go to the emergency department if these symptoms occur.

Intracranial Hypertension

Inform patients that intracranial hypertension has occurred with the use of ORKAMBI. Instruct patients to notify their healthcare provider right away if they experience signs and symptoms of intracranial hypertension, including headache, blurred vision, diplopia, and vision loss [see Warnings and Precautions (5.4)].

Respiratory Events

Inform patients that chest discomfort, dyspnea, and respiration abnormal were more common during initiation of ORKAMBI therapy, especially in patients with advanced lung disease and to contact their healthcare provider if they develop any of these symptoms [see Warnings and Precautions (5.5)].

Effect on Blood Pressure

Inform patients that increased blood pressure has been observed in some patients treated with ORKAMBI and that periodic monitoring of their blood pressure during treatment is recommended and to contact their healthcare provider if they develop elevated blood pressure or notice elevations in pre-existing high blood pressure [see Warnings and Precautions (5.6)].

Drug Interactions with CYP3A Inhibitors and Inducers

- Advise patients to inform their healthcare providers of all concomitant medications, herbal and dietary supplements. Advise patients to avoid grapefruit products during the first week after treatment initiation with ORKAMBI [see Dosage and Administration (2.3), Warnings and Precautions (5.7), and Drug Interactions (7)].
- Instruct post-menarchal patients including females of reproductive potential on alternative methods of birth control because hormonal contraceptives should not be relied upon as an effective method of contraception. ORKAMBI may decrease the effectiveness of hormonal contraceptives and there is an increased incidence of menstruation-related adverse reactions when co-administered with ORKAMBI [see Warnings and Precautions (5.7), Adverse Reactions (6.1), and Drug Interactions (7.11)].

Cataracts

Inform patients that abnormalities of the eye lens (cataract) have been noted in some children and adolescents receiving ORKAMBI. Advise pediatric patients and their caregivers that they will receive ophthalmological examinations before initiating and during ORKAMBI treatment. Advise pediatric patients and/or their caregivers to contact their healthcare provider if they experience visual changes [see Warnings and Precautions (5.8)].

Administration

Inform patients that ORKAMBI should be taken with fat-containing food. A typical CF diet will satisfy this requirement. Examples of fat-containing foods include eggs, avocados, nuts, butter, peanut butter, cheese pizza, breast milk, infant formula, whole-milk dairy products (such as whole milk, cheese, and yogurt), etc. [see Dosage and Administration (2.1) and Clinical Pharmacology (12.3)].

Inform patients and caregivers that ORKAMBI oral granules should be mixed with one teaspoon (5 mL) of age-appropriate soft food or liquid and completely consumed to ensure delivery of the entire dose. Food or liquid should be at or below room temperature. Once mixed, the product has been shown to be stable for one hour, and therefore should be consumed during this period. Some examples of appropriate soft foods or liquids may include puréed fruits or vegetables, flavored yogurt or pudding, applesauce, water, milk, breast milk, infant formula or juice.

Inform patients that if a dose is missed and they remember the missed dose within 6 hours, the patients should take the dose with fat-containing food. If more than 6 hours elapsed after the usual dosing time, the patients should skip that dose and resume the normal schedule for the following dose. Patients should be informed not to take a double dose to make up for the forgotten dose [see Dosage and Administration (2.1)].

Manufactured for
Vertex Pharmaceuticals Incorporated
50 Northern Avenue
Boston, MA 02210

ORKAMBI, the ORKAMBI logo, VERTEX, and the VERTEX triangle logo are registered trademarks of Vertex Pharmaceuticals Incorporated.

All other trademarks referenced herein are the property of their respective owners.

©2025 Vertex Pharmaceuticals Incorporated

ALL RIGHTS RESERVED

PATIENT INFORMATION
ORKAMBI (or-KAM-bee)
(lumacaftor and ivacaftor) tablets for oral use
(lumacaftor and ivacaftor) oral granules

What is ORKAMBI?

- ORKAMBI is a prescription medicine used for the treatment of cystic fibrosis (CF) in people aged 1 year and older who have two copies of the F508del mutation (F508del/F508del) in their CFTR gene.
- ORKAMBI should not be used in people other than those who have two copies of the F508del mutation in their CFTR gene.

It is not known if ORKAMBI is safe and effective in children under 1 year of age.

Before taking ORKAMBI, tell your doctor about all of your medical conditions, including if you:

- have or have had liver problems.
- are allergic to ORKAMBI or any ingredients in ORKAMBI. See the end of this patient information leaflet for a complete list of ingredients in ORKAMBI.
- have kidney problems.
- have lung problems.
- have had an organ transplant.
- are using birth control (hormonal contraceptives, including oral, injectable, transdermal, or implantable forms). Hormonal contraceptives should not be used as a method of birth control when taking ORKAMBI. Talk to your doctor about the best birth control method you should use while taking ORKAMBI.
- are pregnant or plan to become pregnant. It is not known if ORKAMBI will harm your unborn baby. You and your doctor should decide if you will take ORKAMBI while you are pregnant.
- are breastfeeding or planning to breastfeed. It is not known if ORKAMBI passes into your breast milk. You and your doctor should decide if you will take ORKAMBI while you are breastfeeding.

Tell your doctor about all the medicines you take, including prescription and over-the-counter medicines, vitamins, and herbal supplements.

ORKAMBI may affect the way other medicines work, and other medicines may affect how ORKAMBI works. The dose of ORKAMBI may need to be adjusted when taken with certain medicines. Ask your doctor or pharmacist for a list of these medicines if you are not sure.

Especially tell your doctor if you take:

- antibiotics: rifampin (RIFAMATE®, RIFATER®) or rifabutin (MYCOBUTIN®).
- seizure medicines: phenobarbital, carbamazepine (TEGRETOL®, CARBATROL®, EQUETRO®), or phenytoin (DILANTIN®, PHENYTEK®).
- sedatives and anti-anxiety medicines: triazolam (HALCION®) or midazolam (DORMICUM®, HYPNOVEL®, and VERSED®).
- immunosuppressant medicines: cyclosporine, everolimus (ZORTRESS®), sirolimus (RAPAMUNE®), or tacrolimus (ASTAGRAF XL®, ENVARSUS® XR, PROGRAF®, and PROTOPIC®).
- St. John's wort (Hypericum perforatum).
- antifungal medicines including ketoconazole, itraconazole (such as SPORANOX®), posaconazole (such as NOXAFIL®), or voriconazole (such as VFEND®).
- antibiotics including telithromycin, clarithromycin (such as BIAXIN®), or erythromycin (such as ERY-TAB®).

Know the medicines you take. Keep a list of them to show your doctor and pharmacist when you get a new medicine.

How should I take ORKAMBI?

- Take ORKAMBI exactly as your doctor tells you to take it.
- Always take ORKAMBI tablets or granules with foods that contain fat. Examples of fat-containing foods include eggs, avocados, nuts, butter, peanut butter, cheese pizza, breast milk, infant formula, whole-milk dairy products (such as whole milk, cheese, and yogurt).
- Take your doses of ORKAMBI 12 hours apart.
- ORKAMBI tablets (aged 6 years and older):
  - Each ORKAMBI box contains 4 weekly cartons.
  - Each carton contains 7 daily blister strips.
  - Each blister strip contains 4 tablets so you can take 2 tablets for the morning and 2 tablets for the evening.
  - You may cut along the dotted line to separate your morning dose from your evening dose.
  - To take your morning dose, unpeel the paper backing from a blister strip (do not push tablet through backing) to remove 2 ORKAMBI tablets and take them with fat-containing food.
  - 12 hours after your previous dose, open another blister strip (do not push tablet through backing) to remove 2 ORKAMBI tablets and take them with fat-containing food.
- ORKAMBI oral granules (aged 1 to under 6 years old):
  - Hold the packet with the cut line on top.
  - Shake the packet gently to settle the ORKAMBI granules.
  - Tear or cut packet open along cut line.
  - Carefully pour all of the ORKAMBI granules in the packet into one teaspoon (5 mL) of soft food or liquid in a small container (like an empty bowl).
  - The food or liquid should be at or below room temperature. Examples of soft foods or liquids include puréed fruits or vegetables, flavored yogurt or pudding, applesauce, water, milk, breast milk, infant formula or juice.Mix the ORKAMBI granules with food or liquid.
  - After mixing, give ORKAMBI within 1 hour. Make sure all medicine is taken.
  - Give a child fat-containing food just before or just after the ORKAMBI granules dose (see examples above).
- If you miss a dose within 6 hours of when you usually take it, take your dose with fat-containing food as soon as possible.
- If you miss a dose and it is more than 6 hours after the time you usually take it, skip that dose only and take the next dose when you usually take it. Do not take 2 doses at the same time to make up for your missed dose.
- Tell your doctor if you stop ORKAMBI for more than 1-week. Your doctor may need to change your dose of ORKAMBI or other medicines you take.

What should I avoid while taking ORKAMBI?
Do not eat or drink grapefruit products during your first week of treatment with ORKAMBI. Eating or drinking grapefruit products can increase the amount of ORKAMBI in your blood.

What are the possible side effects of ORKAMBI?

ORKAMBI can cause serious side effects, including:

- Worsening of liver function in people with severe liver disease. The worsening of liver function can be serious or cause death. Talk to your doctor if you have been told you have liver disease as your doctor may need to adjust the dose of ORKAMBI.
- High liver enzymes in the blood, which can be a sign of liver injury in people receiving ORKAMBI. Your doctor will do blood tests to check your liver:
  - before you start ORKAMBI
  - every 3 months during your first year of taking ORKAMBI
  - every year while you are taking ORKAMBI

Call your doctor right away if you have any of the following symptoms of liver problems:

- pain or discomfort in the upper right stomach (abdominal) area
- loss of appetite
- dark, amber-colored urine

- yellowing of your skin or the white part of your eyes
- nausea or vomiting
- confusion

- Serious Allergic Reactions can happen to people who are treated with ORKAMBI. Call your doctor or go to the emergency room right away if you have any symptoms of an allergic reaction. Symptoms of an allergic reaction may include:

- rash or hives
- tightness of the chest or throat or difficulty breathing

- swelling of the face, lips, and/or tongue, difficulty swallowing
- light-headedness or dizziness

- Increased pressure around the brain (intracranial hypertension) has happened in people treated with ORKAMBI. If you experience an unusual headache, blurred vision, double vision, or vision loss, call your doctor right away.
- Breathing problems such as trouble breathing, shortness of breath or chest tightness in people when starting ORKAMBI, especially in people who have poor lung function. If you have poor lung function, your doctor may monitor you more closely when you start ORKAMBI. Call your doctor right away if you have trouble breathing, shortness of breath or chest tightness.
- An increase in blood pressure in some people receiving ORKAMBI. Your doctor should monitor your blood pressure during treatment with ORKAMBI. Call your doctor right away if you have an increase in blood pressure.
- Abnormality of the eye lens (cataract) in some children and adolescents receiving ORKAMBI. If you are a child or adolescent, your doctor should perform eye examinations before and during treatment with ORKAMBI to look for cataracts.

The most common side effects of ORKAMBI include:

- breathing problems such as shortness of breath and chest tightness
- nausea
- diarrhea
- fatigue
- increase in a certain blood enzyme called creatine phosphokinase

- rash
- gas
- common cold, including sore throat, stuffy or runny nose
- flu or flu-like symptoms
- irregular, missed, or abnormal periods (menses) and increase in the amount of menstrual bleeding

Additional side effects in children

Side effects seen in children are similar to those seen in adults and adolescents. Additional common side effects seen in children include:

- cough with sputum
- stuffy nose
- headache

- stomach pain
- increase in sputum

Tell your doctor if you have any side effect that bothers you or that does not go away.
These are not all the possible side effects of ORKAMBI. Call your doctor for medical advice about side effects. You may report side effects to FDA at 1-800-FDA-1088.

How should I store ORKAMBI?

- Store ORKAMBI at room temperature between 68°F to 77°F (20°C to 25°C).

Keep ORKAMBI and all medicines out of the reach of children.

General information about the safe and effective use of ORKAMBI.

Medicines are sometimes prescribed for purposes other than those listed in a Patient Information leaflet. Do not use ORKAMBI for a condition for which it was not prescribed. Do not give ORKAMBI to other people, even if they have the same symptoms you have. It may harm them.

You can ask your pharmacist or doctor for information about ORKAMBI that is written for health professionals.

What are the ingredients in ORKAMBI?

ORKAMBI tablets:
Active ingredients: lumacaftor and ivacaftor
Inactive ingredients: cellulose, microcrystalline; croscarmellose sodium; hypromellose acetate succinate; magnesium stearate; povidone; and sodium lauryl sulfate.

The tablet film coat contains: carmine, FD&C Blue #1, FD&C Blue #2, polyethylene glycol, polyvinyl alcohol, talc, and titanium dioxide.

The printing ink contains: ammonium hydroxide, iron oxide black, propylene glycol, and shellac.
ORKAMBI oral granules
Active ingredients: lumacaftor and ivacaftor
Inactive ingredients: cellulose, microcrystalline; croscarmellose sodium; hypromellose acetate succinate; povidone; and sodium lauryl sulfate.

Manufactured for: Vertex Pharmaceuticals Incorporated; 50 Northern Avenue, Boston, MA 02210
For more information, go to www.orkambi.com or call 1-877-752-5933.
ORKAMBI, the ORKAMBI logo, VERTEX, and the VERTEX triangle logo are registered trademarks of Vertex Pharmaceuticals Incorporated.
All other trademarks referenced herein are the property of their respective owners.
©2025 Vertex Pharmaceuticals Incorporated

This Patient Information has been approved by the U.S. Food and Drug Administration.

Revised: 09/2025

PRINCIPAL DISPLAY PANEL - 200 mg/125 mg Tablet Blister Pack Carton Box

Rx only
NDC 51167-809-01

ORKAMBI®
(Lumacaftor/Ivacaftor) tablets
200 mg/125 mg per tablet

112 tablets

PRINCIPAL DISPLAY PANEL - 100 mg/125 mg Tablet Blister Pack Carton Box

Rx only
NDC 51167-700-02

ORKAMBI®
(Lumacaftor/Ivacaftor) tablets
100 mg/125 mg per tablet

112 tablets

PRINCIPAL DISPLAY PANEL - 100 mg/125 mg Granule Packet Carton

Rx only
NDC 51167-900-01

ORKAMBI®
(Lumacaftor/Ivacaftor)

100 mg
125 mg

Oral Granules
100 mg/125 mg per packet

56 packets
Carton contains: 4 individual wallets
with 14 packets per wallet

Lift here to open

PRINCIPAL DISPLAY PANEL - 150 mg/188 mg Granule Packet Carton

Rx only

NDC 51167-500-02

ORKAMBI®
(Lumacaftor/Ivacaftor)

150 mg
188 mg

Oral Granules
150 mg/188 mg per packet

56 packets
Carton contains: 4 individual wallets
with 14 packets per wallet

Lift here to open

PRINCIPAL DISPLAY PANEL - 75 mg/94 mg Granule Packet Carton

Rx only

NDC 51167-122-01

ORKAMBI®
(Lumacaftor/Ivacaftor)

75 mg
94 mg

Oral Granules
75 mg/94 mg per packet

56 packets
Carton contains: 4 individual wallets
with 14 packets per wallet

Lift here to open